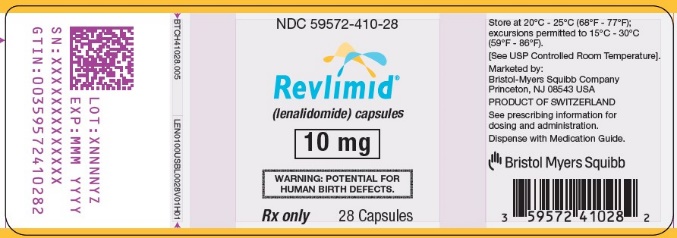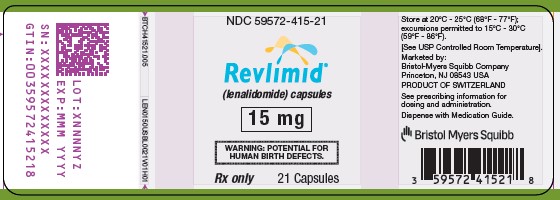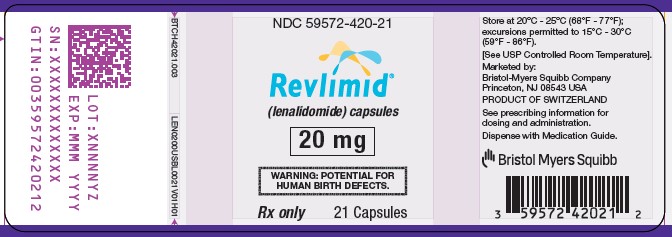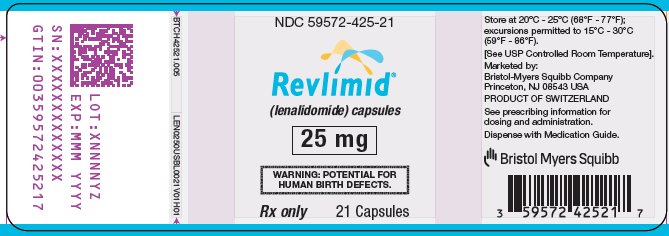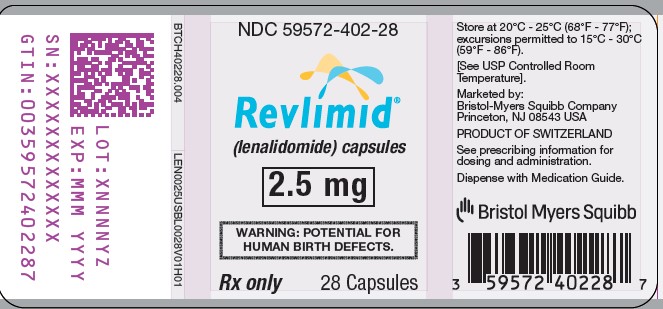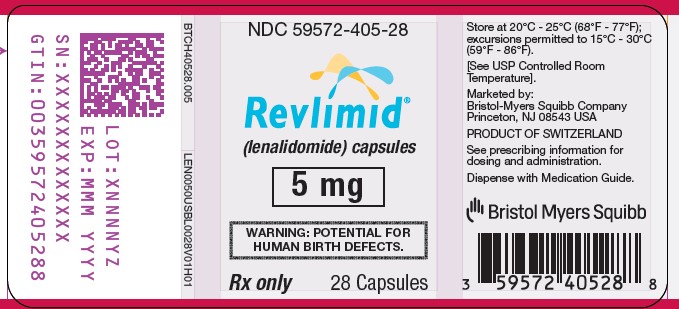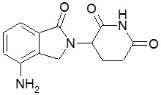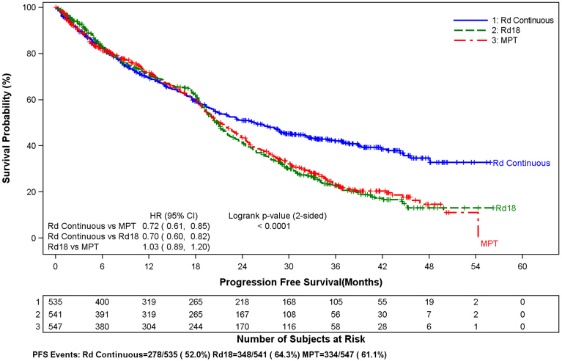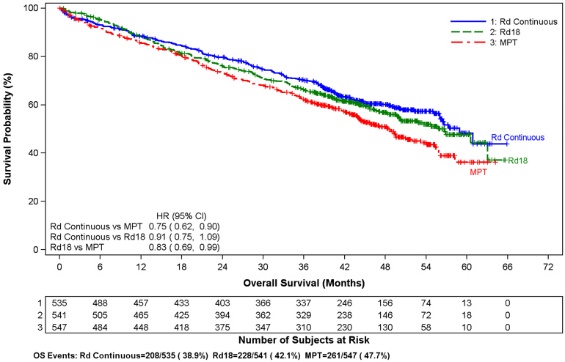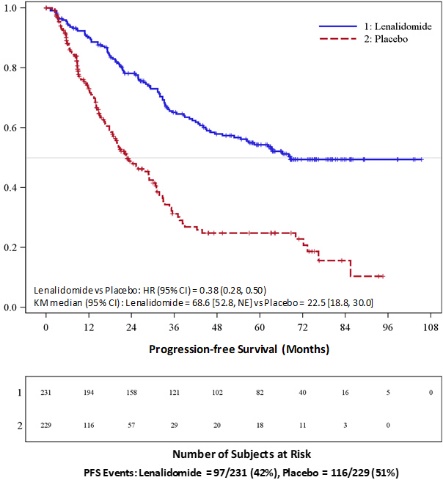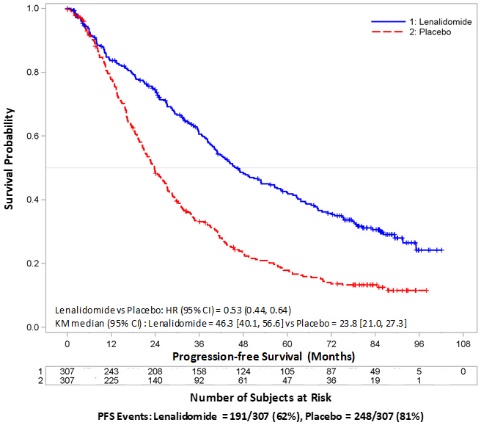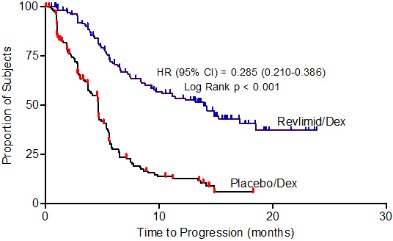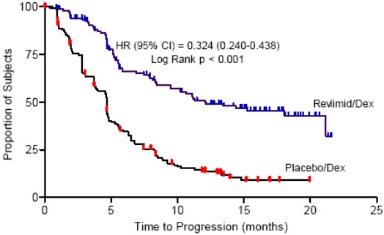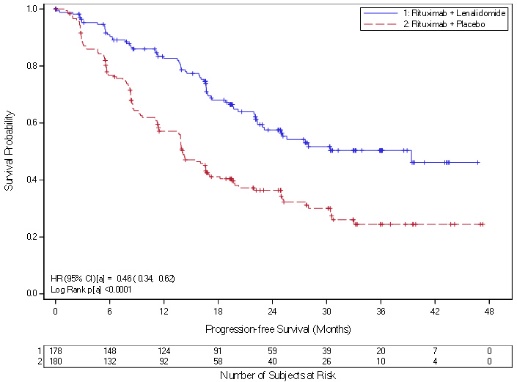 DRUG LABEL: Revlimid
NDC: 59572-402 | Form: CAPSULE
Manufacturer: Celgene Corporation
Category: prescription | Type: HUMAN PRESCRIPTION DRUG LABEL
Date: 20230324

ACTIVE INGREDIENTS: LENALIDOMIDE 2.5 mg/1 1
INACTIVE INGREDIENTS: ANHYDROUS LACTOSE; MICROCRYSTALLINE CELLULOSE; CROSCARMELLOSE SODIUM; MAGNESIUM STEARATE

HIGHLIGHTS OF PRESCRIBING INFORMATION

These highlights do not include all the information needed to use REVLIMID® safely and effectively. See full prescribing information for REVLIMID.
REVLIMID (lenalidomide) capsules, for oral use
Initial U.S. Approval: 2005

RECENT MAJOR CHANGES

Warnings and Precautions (5.1, 5.2) | 8/2021
Warnings and Precautions (5.1, 5.11) | 5/2022

WARNING: EMBRYO-FETAL TOXICITY, HEMATOLOGIC TOXICITY, and VENOUS and ARTERIAL THROMBOEMBOLISM

See full prescribing information for complete boxed warning.

EMBRYO-FETAL TOXICITY

- Lenalidomide, a thalidomide analogue, caused limb abnormalities in a developmental monkey study similar to birth defects caused by thalidomide in humans. If lenalidomide is used during pregnancy, it may cause birth defects or embryo-fetal death.
- Pregnancy must be excluded before start of treatment. Prevent pregnancy during treatment by the use of two reliable methods of contraception (5.1).

REVLIMID is available only through a restricted distribution program, called the Lenalidomide REMS program (5.2, 17).

HEMATOLOGIC TOXICITY. REVLIMID can cause significant neutropenia and thrombocytopenia (5.3).

VENOUS AND ARTERIAL THROMBOEMBOLISM

Significantly increased risk of deep vein thrombosis (DVT) and pulmonary embolism (PE), as well as risk of myocardial infarction and stroke in patients with multiple myeloma receiving REVLIMID with dexamethasone. Anti-thrombotic prophylaxis is recommended (5.4).

1 INDICATIONS AND USAGE

REVLIMID is a thalidomide analogue indicated for the treatment of adult patients with:

- Multiple myeloma (MM), in combination with dexamethasone (1.1).
- MM, as maintenance following autologous hematopoietic stem cell transplantation (auto-HSCT) (1.1).
- Transfusion-dependent anemia due to low- or intermediate-1-risk myelodysplastic syndromes (MDS) associated with a deletion 5q abnormality with or without additional cytogenetic abnormalities (1.2).
- Mantle cell lymphoma (MCL) whose disease has relapsed or progressed after two prior therapies, one of which included bortezomib (1.3).
- Previously treated follicular lymphoma (FL), in combination with a rituximab product (1.4).
- Previously treated marginal zone lymphoma (MZL), in combination with a rituximab product (1.5).

Limitations of Use:

- REVLIMID is not indicated and is not recommended for the treatment of patients with chronic lymphocytic leukemia (CLL) outside of controlled clinical trials (1.4).

2 DOSAGE AND ADMINISTRATION

- MM combination therapy: 25 mg once daily orally on Days 1-21 of repeated 28-day cycles. (2.1).
- MM maintenance therapy following auto-HSCT: 10 mg once daily continuously on Days 1-28 of repeated 28-day cycles (2.1).
- MDS: 10 mg once daily (2.2).
- MCL: 25 mg once daily orally on Days 1-21 of repeated 28-day cycles (2.3).
- FL or MZL: 20 mg once daily orally on Days 1-21 of repeated 28-day cycles for up to 12 cycles (2.4).
- Renal impairment: Adjust starting dose based on the creatinine clearance value (2.6).
- For concomitant therapy doses, see Full Prescribing Information (2.1, 2.4, 14.1, 14.4).

3 DOSAGE FORMS AND STRENGTHS

Capsules: 2.5 mg, 5 mg, 10 mg, 15 mg, 20 mg, and 25 mg (3).

4 CONTRAINDICATIONS

- Pregnancy (Boxed Warning, 4.1, 5.1, 8.1).
- Demonstrated severe hypersensitivity to lenalidomide (4.2, 5.9, 5.15).

5 WARNINGS AND PRECAUTIONS

- Increased Mortality: serious and fatal cardiac adverse reactions occurred in patients with CLL treated with REVLIMID (5.5).
- Second Primary Malignancies (SPM): Higher incidences of SPM were observed in controlled trials of patients with MM receiving REVLIMID (5.6).
- Increased Mortality: Observed in patients with MM when pembrolizumab was added to dexamethasone and a thalidomide analogue (5.7).
- Hepatotoxicity: Hepatic failure including fatalities; monitor liver function. Stop REVLIMID and evaluate if hepatotoxicity is suspected (5.8).
- Severe Cutaneous Reactions: Discontinue REVLIMID for severe reactions (5.9).
- Tumor lysis syndrome (TLS) including fatalities: Monitor patients at risk of TLS (i.e., those with high tumor burden) and take appropriate precautions (5.10).
- Tumor flare reaction: Serious tumor flare reactions, including fatal reactions, have occurred during investigational use of REVLIMID for chronic lymphocytic leukemia and lymphoma (5.11).
- Impaired Stem Cell mobilization: A decrease in the number of CD34+ cells collected after treatment (> 4 cycles) with REVLIMID has been reported. Consider early referral to transplant center (5.12).
- Early mortality in MCL: Higher rate of early deaths have occurred in patients with MCL (5.14).
- Hypersensitivity: Monitor patients for potential hypersensitivity. Discontinue REVLIMID for angioedema and anaphylaxis (5.15).

6 ADVERSE REACTIONS

- MM: Most common adverse reactions (≥20%) include diarrhea, fatigue, anemia, constipation, neutropenia, leukopenia, peripheral edema, insomnia, muscle cramp/spasms, abdominal pain, back pain, nausea, asthenia, pyrexia, upper respiratory tract infection, bronchitis, nasopharyngitis, gastroenteritis, cough, rash, dyspnea, dizziness, decreased appetite, thrombocytopenia, and tremor (6.1).
- MDS: Most common adverse reactions (>15%) include thrombocytopenia, neutropenia, diarrhea, pruritus, rash, fatigue, constipation, nausea, nasopharyngitis, arthralgia, pyrexia, back pain, peripheral edema, cough, dizziness, headache, muscle cramp, dyspnea, pharyngitis, and epistaxis (6.1).
- Non-Hodgkin's Lymphoma (NHL: MCL, FL or MZL): Most common adverse reactions (≥15%) included neutropenia, thrombocytopenia, anemia, leukopenia, diarrhea, constipation, nausea, fatigue, pyrexia, cough, upper respiratory tract infection, and rash (6.1).

To report SUSPECTED ADVERSE REACTIONS, contact Bristol-Myers Squibb at 1-800-721-5072 or FDA at 1-800-FDA-1088 or www.fda.gov/medwatch.

7 DRUG INTERACTIONS

- Digoxin: Monitor digoxin plasma levels periodically due to increased Cmax and AUC with concomitant REVLIMID therapy (7.1).
- Concomitant use of erythropoietin stimulating agents or estrogen containing therapies with REVLIMID may increase the risk of thrombosis (7.2).

8 USE IN SPECIFIC POPULATIONS

- Lactation: Advise not to breastfeed (8.2).

FULL PRESCRIBING INFORMATION

WARNING: EMBRYO-FETAL TOXICITY, HEMATOLOGIC TOXICITY, and VENOUS and ARTERIAL THROMBOEMBOLISM

Embryo-Fetal Toxicity

Do not use REVLIMID during pregnancy. Lenalidomide, a thalidomide analogue, caused limb abnormalities in a developmental monkey study. Thalidomide is a known human teratogen that causes severe life-threatening human birth defects. If lenalidomide is used during pregnancy, it may cause birth defects or embryo-fetal death. In females of reproductive potential, obtain 2 negative pregnancy tests before starting REVLIMID® treatment. Females of reproductive potential must use 2 forms of contraception or continuously abstain from heterosexual sex during and for 4 weeks after REVLIMID treatment [see Warnings and Precautions (5.1), and Medication Guide (17)]. To avoid embryo-fetal exposure to lenalidomide, REVLIMID is only available through a restricted distribution program, the Lenalidomide REMS program (5.2).

Information about the Lenalidomide REMS program is available at www.lenalidomiderems.com or by calling the REMS Call Center at 1-888-423-5436.

Hematologic Toxicity (Neutropenia and Thrombocytopenia)

REVLIMID can cause significant neutropenia and thrombocytopenia. Eighty percent of patients with del 5q myelodysplastic syndromes had to have a dose delay/reduction during the major study. Thirty-four percent of patients had to have a second dose delay/reduction. Grade 3 or 4 hematologic toxicity was seen in 80% of patients enrolled in the study. Patients on therapy for del 5q myelodysplastic syndromes should have their complete blood counts monitored weekly for the first 8 weeks of therapy and at least monthly thereafter. Patients may require dose interruption and/or reduction. Patients may require use of blood product support and/or growth factors [see Dosage and Administration (2.2)].

Venous and Arterial Thromboembolism

REVLIMID has demonstrated a significantly increased risk of deep vein thrombosis (DVT) and pulmonary embolism (PE), as well as risk of myocardial infarction and stroke in patients with multiple myeloma who were treated with REVLIMID and dexamethasone therapy. Monitor for and advise patients about signs and symptoms of thromboembolism. Advise patients to seek immediate medical care if they develop symptoms such as shortness of breath, chest pain, or arm or leg swelling. Thromboprophylaxis is recommended and the choice of regimen should be based on an assessment of the patient’s underlying risks [see Warnings and Precautions (5.4)].

1 INDICATIONS AND USAGE

1.1 Multiple Myeloma

REVLIMID in combination with dexamethasone is indicated for the treatment of adult patients with multiple myeloma (MM).

REVLIMID is indicated as maintenance therapy in adult patients with MM following autologous hematopoietic stem cell transplantation (auto-HSCT).

1.2 Myelodysplastic Syndromes

REVLIMID is indicated for the treatment of adult patients with transfusion-dependent anemia due to low- or intermediate-1-risk myelodysplastic syndromes (MDS) associated with a deletion 5q cytogenetic abnormality with or without additional cytogenetic abnormalities.

1.3 Mantle Cell Lymphoma

REVLIMID is indicated for the treatment of adult patients with mantle cell lymphoma (MCL) whose disease has relapsed or progressed after two prior therapies, one of which included bortezomib.

1.4 Follicular Lymphoma

REVLIMID in combination with a rituximab product, is indicated for the treatment of adult patients with previously treated follicular lymphoma (FL).

1.5 Marginal Zone Lymphoma

REVLIMID in combination with a rituximab product, is indicated for the treatment of adult patients with previously treated marginal zone lymphoma (MZL).

1.6 Limitations of Use

REVLIMID is not indicated and is not recommended for the treatment of patients with CLL outside of controlled clinical trials [see Warnings and Precautions (5.5)].

2 DOSAGE AND ADMINISTRATION

2.1 Recommended Dosage for Multiple Myeloma

REVLIMID Combination Therapy

The recommended starting dose of REVLIMID is 25 mg orally once daily on Days 1-21 of repeated 28-day cycles in combination with dexamethasone. Refer to Section 14.1 for specific dexamethasone dosing. For patients greater than 75 years old, the starting dose of dexamethasone may be reduced [see Clinical Studies (14.1)]. Treatment should be continued until disease progression or unacceptable toxicity.

In patients who are not eligible for auto-HSCT, treatment should continue until disease progression or unacceptable toxicity. For patients who are auto-HSCT-eligible, hematopoietic stem cell mobilization should occur within 4 cycles of a REVLIMID-containing therapy [see Warnings and Precautions (5.12)].

Dose Adjustments for Hematologic Toxicities During MM Treatment

Dose modification guidelines, as summarized in Table 1 below, are recommended to manage Grade 3 or 4 neutropenia or thrombocytopenia or other Grade 3 or 4 toxicity judged to be related to REVLIMID.

Table 1: Dose Adjustments for Hematologic Toxicities for MM
Platelet counts
 | Thrombocytopenia in MM
 | When Platelets | Recommended Course Days 1-21 of repeated 28-day cycle
 | Fall below 30,000/mcL | Interrupt REVLIMID treatment, follow CBC weekly
 | Return to at least 30,000/mcL | Resume REVLIMID at next lower dose. Do not dose below 2.5 mg daily
 | For each subsequent drop below 30,000/mcL | Interrupt REVLIMID treatment
 | Return to at least 30,000/mcL | Resume REVLIMID at next lower dose. Do not dose below 2.5 mg daily
Absolute Neutrophil counts (ANC)
 | Neutropenia in MM
 | When Neutrophils | Recommended Course Days 1-21 of repeated 28-day cycle
 | Fall below 1,000/mcL | Interrupt REVLIMID treatment, follow CBC weekly
 | Return to at least 1,000/mcL and neutropenia is the only toxicity | Resume REVLIMID at 25 mg daily or initial starting dose
 | Return to at least 1,000/mcL and if other toxicity | Resume REVLIMID at next lower dose. Do not dose below 2.5 mg daily
 | For each subsequent drop below 1,000/mcL | Interrupt REVLIMID treatment
 | Return to at least 1,000/mcL | Resume REVLIMID at next lower dose. Do not dose below 2.5 mg daily

REVLIMID Maintenance Therapy Following Auto-HSCT

Following auto-HSCT, initiate REVLIMID maintenance therapy after adequate hematologic recovery (ANC at least 1,000/mcL and/or platelet counts at least 75,000/mcL). The recommended starting dose of REVLIMID is 10 mg once daily continuously (Days 1-28 of repeated 28-day cycles) until disease progression or unacceptable toxicity. After 3 cycles of maintenance therapy, the dose can be increased to 15 mg once daily if tolerated.

Dose Adjustments for Hematologic Toxicities During MM Treatment

Dose modification guidelines, as summarized in Table 2 below, are recommended to manage Grade 3 or 4 neutropenia or thrombocytopenia or other Grade 3 or 4 toxicity judged to be related to REVLIMID.

Table 2: Dose Adjustments for Hematologic Toxicities for MM
Platelet counts
 | Thrombocytopenia in MM
 | When Platelets | Recommended Course
 | Fall below 30,000/mcL | Interrupt REVLIMID treatment, follow CBC weekly
 | Return to at least 30,000/mcL | Resume REVLIMID at next lower dose, continuously for Days 1-28 of repeated 28-day cycle
 | If at the 5 mg daily dose, For a subsequent drop below 30,000/mcL | Interrupt REVLIMID treatment. Do not dose below 5 mg daily for Day 1 to 21 of 28 day cycle
 | Return to at least 30,000/mcL | Resume REVLIMID at 5 mg daily for Days 1 to 21 of 28-day cycle. Do not dose below 5 mg daily for Day 1 to 21 of 28 day cycle
Absolute Neutrophil counts (ANC)
 | Neutropenia in MM
 | When Neutrophils | Recommended Course
 | Fall below 500/mcL | Interrupt REVLIMID treatment, follow CBC weekly
 | Return to at least 500/mcL | Resume REVLIMID at next lower dose, continuously for Days 1-28 of repeated 28-day cycle
 | If at 5 mg daily dose, For a subsequent drop below 500/mcL | Interrupt REVLIMID treatment. Do not dose below 5 mg daily for Days 1 to 21 of 28-day cycle
 | Return to at least 500/mcL | Resume REVLIMID at 5 mg daily for Days 1 to 21 of 28-day cycle. Do not dose below 5 mg daily for Days 1 to 21 of 28-day cycle

2.2 Recommended Dosage for Myelodysplastic Syndromes

The recommended starting dose of REVLIMID is 10 mg daily. Treatment is continued or modified based upon clinical and laboratory findings. Continue treatment until disease progression or unacceptable toxicity.

Dose Adjustments for Hematologic Toxicities During MDS Treatment

Patients who are dosed initially at 10 mg and who experience thrombocytopenia should have their dosage adjusted as follows:

Platelet counts

If thrombocytopenia develops WITHIN 4 weeks of starting treatment at 10 mg daily in MDS

If baseline is at least 100,000/mcL
When Platelets | Recommended Course
Fall below 50,000/mcL | Interrupt REVLIMID treatment
Return to at least 50,000/mcL | Resume REVLIMID at 5 mg daily
If baseline is below 100,000/mcL
When Platelets | Recommended Course
Fall to 50% of the baseline value | Interrupt REVLIMID treatment
If baseline is at least 60,000/mcL and returns to at least 50,000/mcL | Resume REVLIMID at 5 mg daily
If baseline is below 60,000/mcL and returns to at least 30,000/mcL | Resume REVLIMID at 5 mg daily

If thrombocytopenia develops AFTER 4 weeks of starting treatment at 10 mg daily in MDS

When Platelets | Recommended Course
Fall below 30,000/mcL or below 50,000/mcL with platelet transfusions | Interrupt REVLIMID treatment
Return to at least 30,000/mcL (without hemostatic failure) | Resume REVLIMID at 5 mg daily

Patients who experience thrombocytopenia at 5 mg daily should have their dosage adjusted as follows:

If thrombocytopenia develops during treatment at 5 mg daily in MDS

When Platelets | Recommended Course
Fall below 30,000/mcL or below 50,000/mcL with platelet transfusions | Interrupt REVLIMID treatment
Return to at least 30,000/mcL (without hemostatic failure) | Resume REVLIMID at 2.5 mg daily

Patients who are dosed initially at 10 mg and experience neutropenia should have their dosage adjusted as follows:

Absolute Neutrophil counts (ANC)

If neutropenia develops WITHIN 4 weeks of starting treatment at 10 mg daily in MDS

If baseline ANC is at least 1,000/mcL
When Neutrophils | Recommended Course
Fall below 750/mcL | Interrupt REVLIMID treatment
Return to at least 1,000/mcL | Resume REVLIMID at 5 mg daily
If baseline ANC is below 1,000/mcL
When Neutrophils | Recommended Course
Fall below 500/mcL | Interrupt REVLIMID treatment
Return to at least 500/mcL | Resume REVLIMID at 5 mg daily

If neutropenia develops AFTER 4 weeks of starting treatment at 10 mg daily in MDS

When Neutrophils | Recommended Course
Fall below 500/mcL for at least 7 days or below 500/mcL associated with fever (at least 38.5°C) | Interrupt REVLIMID treatment
Return to at least 500/mcL | Resume REVLIMID at 5 mg daily

Patients who experience neutropenia at 5 mg daily should have their dosage adjusted as follows:

If neutropenia develops during treatment at 5 mg daily in MDS

When Neutrophils | Recommended Course
Fall below 500/mcL for at least 7 days or below 500/mcL associated with fever (at least 38.5°C) | Interrupt REVLIMID treatment
Return to at least 500/mcL | Resume REVLIMID at 2.5 mg daily

2.3 Recommended Dosage for Mantle Cell Lymphoma

The recommended starting dose of REVLIMID is 25 mg/day orally on Days 1-21 of repeated 28-day cycles for relapsed or refractory mantle cell lymphoma. Treatment should be continued until disease progression or unacceptable toxicity.

Treatment is continued, modified or discontinued based upon clinical and laboratory findings.

Dose Adjustments for Hematologic Toxicities During MCL Treatment

Dose modification guidelines as summarized below are recommended to manage Grade 3 or 4 neutropenia or thrombocytopenia or other Grade 3 or 4 toxicities considered to be related to REVLIMID.

Platelet counts

Thrombocytopenia during treatment in MCL

When Platelets | Recommended Course
Fall below 50,000/mcL | Interrupt REVLIMID treatment and follow CBC weekly
Return to at least 50,000/mcL | Resume REVLIMID at 5 mg less than the previous dose. Do not dose below 5 mg daily

Absolute Neutrophil counts (ANC)

Neutropenia during treatment in MCL

When Neutrophils | Recommended Course
Fall below 1,000/mcL for at least 7 days OR Falls below 1,000/mcL with an associated temperature at least 38.5°C OR Falls below 500/mcL | Interrupt REVLIMID treatment and follow CBC weekly
Return to at least 1,000/mcL | Resume REVLIMID at 5 mg less than the previous dose. Do not dose below 5 mg daily

2.4 Recommended Dosage for Follicular Lymphoma or Marginal Zone Lymphoma

The recommended starting dose of REVLIMID is 20 mg orally once daily on Days 1-21 of repeated 28-day cycles for up to 12 cycles of treatment in combination with a rituximab-product. Refer to Section 14.4 for specific rituximab dosing from the AUGMENT trial. For dose adjustments due to toxicity with rituximab, refer to the product prescribing information.

Dose Adjustments for Hematologic Toxicities during FL or MZL Treatment

Dose modification guidelines, as summarized below, are recommended to manage Grade 3 or 4 neutropenia or thrombocytopenia or other Grade 3 or 4 toxicity judged to be related to REVLIMID.

Platelet counts

Thrombocytopenia during treatment in FL or MZL

When Platelets | Recommended Course
Fall below 50,000/mcL | Interrupt REVLIMID treatment and follow CBC weekly.
Return to at least 50,000/mcL | If patient starting dose was 20 mg daily, resume REVLIMID at 5 mg less than the previous dose. Do not dose below 5 mg daily. If patient starting dose was 10 mg daily, resume at 5 mg less than previous dose. Do not dose below 2.5 mg daily.

Absolute Neutrophil counts (ANC)

Neutropenia during treatment in FL or MZL

When Neutrophils | Recommended Course
Fall below 1,000/mcL for at least 7 days OR Falls below 1,000/mcL with an associated temperature at least 38.5°C OR Falls below 500/mcL | Interrupt REVLIMID treatment and follow CBC weekly.
Return to at least 1,000/mcL | If patient starting dose was 20 mg daily, resume REVLIMID at 5 mg less than the previous dose. Do not dose below 5 mg daily. If patient starting dose was 10 mg daily, resume at 5 mg less than previous dose. Do not dose below 2.5 mg daily.

2.5 Dosage Modifications for Non-Hematologic Adverse Reactions

For non-hematologic Grade 3/4 toxicities judged to be related to REVLIMID, hold treatment and restart at the physician's discretion at next lower dose level when toxicity has resolved to Grade 2 or below.

Permanently discontinue REVLIMID for angioedema, anaphylaxis, Grade 4 rash, skin exfoliation, bullae, or any other severe dermatologic reactions [see Warnings and Precautions (5.9, 5.15)].

2.6 Recommended Dosage for Patients with Renal Impairment

The recommendations for dosing patients with renal impairment are shown in the following table [see Clinical Pharmacology (12.3)].

Table 3: Dose Adjustments for Patients with Renal Impairment
Renal Function (Cockcroft-Gault) | Dose in REVLIMID Combination Therapy for MM and MCL | Dose in REVLIMID Combination Therapy for FL and MZL | Dose in REVLIMID Maintenance Therapy Following Auto-HSCT for MM and for MDS
CLcr 30 to 60 mL/min | 10 mg once daily | 10 mg once daily | 5 mg once daily
CLcr below 30 mL/min (not requiring dialysis) | 15 mg every other day | 5 mg once daily | 2.5 mg once daily
CLcr below 30 mL/min (requiring dialysis) | 5 mg once daily. On dialysis days, administer the dose following dialysis. | 5 mg once daily. On dialysis days, administer the dose following dialysis. | 2.5 mg once daily. On dialysis days, administer the dose following dialysis.

REVLIMID Combination Therapy for MM: For CLcr of 30 to 60 mL/min, consider escalating the dose to 15 mg after 2 cycles if the patient tolerates the 10 mg dose of lenalidomide without dose-limiting toxicity.

REVLIMID Maintenance Therapy Following Auto-HSCT for MM and for MCL and MDS: Base subsequent REVLIMID dose increase or decrease on individual patient treatment tolerance [see Dosage and Administration (2.1- 2.3)].

REVLIMID Combination Therapy for FL or for MZL: For patients with CLcr of 30 to 60 mL/min, after 2 cycles, the REVLIMID dose may be increased to 15 mg orally if the patient has tolerated therapy.

2.7 Administration

Advise patients to take REVLIMID orally at about the same time each day, either with or without food. Advise patients to swallow REVLIMID capsules whole with water and not to open, break, or chew them.

3 DOSAGE FORMS AND STRENGTHS

Capsules:

- 2.5 mg, white and blue-green opaque hard capsules imprinted "REV" on one half and "2.5 mg" on the other half in black ink
- 5 mg, white opaque capsules imprinted "REV" on one half and "5 mg" on the other half in black ink
- 10 mg, blue/green and pale yellow opaque capsules imprinted "REV" on one half and "10 mg" on the other half in black ink
- 15 mg, powder blue and white opaque capsules imprinted "REV" on one half and "15 mg" on the other half in black ink
- 20 mg, powder blue and blue-green opaque hard capsules imprinted "REV" on one half and "20 mg" on the other half in black ink
- 25 mg, white opaque capsules imprinted "REV" on one half and "25 mg" on the other half in black ink

4 CONTRAINDICATIONS

4.1 Pregnancy

REVLIMID can cause fetal harm when administered to a pregnant female. Limb abnormalities were seen in the offspring of monkeys that were dosed with lenalidomide during organogenesis. This effect was seen at all doses tested. Due to the results of this developmental monkey study, and lenalidomide's structural similarities to thalidomide, a known human teratogen, lenalidomide is contraindicated in females who are pregnant [see Boxed Warning]. If this drug is used during pregnancy or if the patient becomes pregnant while taking this drug, the patient should be apprised of the potential risk to a fetus [see Warnings and Precautions (5.1, 5.2), Use in Special Populations (8.1, 8.3)].

4.2 Severe Hypersensitivity Reactions

REVLIMID is contraindicated in patients who have demonstrated severe hypersensitivity (e.g., angioedema, Stevens-Johnson syndrome, toxic epidermal necrolysis) to lenalidomide [see Warnings and Precautions (5.9, 5.15)].

5 WARNINGS AND PRECAUTIONS

5.1 Embryo-Fetal Toxicity

REVLIMID is a thalidomide analogue and is contraindicated for use during pregnancy. Thalidomide is a known human teratogen that causes life-threatening human birth defects or embryo-fetal death [see Use in Specific Populations (8.1)]. An embryo-fetal development study in monkeys indicates that lenalidomide produced malformations in the offspring of female monkeys who received the drug during pregnancy, similar to birth defects observed in humans following exposure to thalidomide during pregnancy.

REVLIMID is only available through the Lenalidomide REMS program [see Warnings and Precautions (5.2)].

Females of Reproductive Potential

Females of reproductive potential must avoid pregnancy for at least 4 weeks before beginning REVLIMID therapy, during therapy, during dose interruptions and for at least 4 weeks after completing therapy.

Females must commit either to abstain continuously from heterosexual sexual intercourse or to use two methods of reliable birth control, beginning 4 weeks prior to initiating treatment with REVLIMID, during therapy, during dose interruptions and continuing for 4 weeks following discontinuation of REVLIMID therapy.

Two negative pregnancy tests must be obtained prior to initiating therapy. The first test should be performed within 10-14 days and the second test within 24 hours prior to prescribing REVLIMID therapy and then weekly during the first month, then monthly thereafter in females with regular menstrual cycles or every 2 weeks in females with irregular menstrual cycles [see Use in Specific Populations (8.3)].

Males

Lenalidomide is present in the semen of patients receiving the drug. Therefore, males must always use a latex or synthetic condom during any sexual contact with females of reproductive potential while taking REVLIMID and for up to 4 weeks after discontinuing REVLIMID, even if they have undergone a successful vasectomy. Male patients taking REVLIMID must not donate sperm and for up to 4 weeks after discontinuing REVLIMID [see Use in Specific Populations (8.3)].

Blood Donation

Patients must not donate blood during treatment with REVLIMID and for 4 weeks following discontinuation of the drug because the blood might be given to a pregnant female patient whose fetus must not be exposed to REVLIMID.

5.2 Lenalidomide REMS Program

Because of the embryo-fetal risk [see Warnings and Precautions (5.1)], REVLIMID is available only through a restricted program under a Risk Evaluation and Mitigation Strategy (REMS), the Lenalidomide REMS program.

Required components of the Lenalidomide REMS program include the following:

- Prescribers must be certified with the Lenalidomide REMS program by enrolling and complying with the REMS requirements.
- Patients must sign a Patient-Physician agreement form and comply with the REMS requirements. In particular, female patients of reproductive potential who are not pregnant must comply with the pregnancy testing and contraception requirements [see Use in Specific Populations (8.3)] and males must comply with contraception requirements [see Use in Specific Populations (8.3)].
- Pharmacies must be certified with the Lenalidomide REMS program, must only dispense to patients who are authorized to receive REVLIMID and comply with REMS requirements.

Further information about the Lenalidomide REMS program is available at www.lenalidomiderems.com or by telephone at 1-888-423-5436.

5.3 Hematologic Toxicity

REVLIMID can cause significant neutropenia and thrombocytopenia. Monitor patients with neutropenia for signs of infection. Advise patients to observe for bleeding or bruising, especially with use of concomitant medication that may increase risk of bleeding. Patients taking REVLIMID should have their complete blood counts assessed periodically as described below [see Dosage and Administration (2.1, 2.2, 2.3)].

Monitor complete blood counts (CBC) in patients taking REVLIMID in combination with dexamethasone or as REVLIMID maintenance therapy for MM every 7 days (weekly) for the first 2 cycles, on Days 1 and 15 of Cycle 3, and every 28 days (4 weeks) thereafter. A dose interruption and/or dose reduction may be required [see Dosage and Administration (2.1)]. In the MM maintenance therapy trials, Grade 3 or 4 neutropenia was reported in up to 59% of REVLIMID-treated patients and Grade 3 or 4 thrombocytopenia in up to 38% of REVLIMID-treated patients [see Adverse Reactions (6.1)].

Monitor complete blood counts (CBC) in patients taking REVLIMID for MDS weekly for the first 8 weeks and at least monthly thereafter. Grade 3 or 4 hematologic toxicity was seen in 80% of patients enrolled in the MDS study. In the 48% of patients who developed Grade 3 or 4 neutropenia, the median time to onset was 42 days (range, 14-411 days), and the median time to documented recovery was 17 days (range, 2-170 days). In the 54% of patients who developed Grade 3 or 4 thrombocytopenia, the median time to onset was 28 days (range, 8-290 days), and the median time to documented recovery was 22 days (range, 5-224 days) [see Boxed Warning and Dosage and Administration (2.2)].

Monitor complete blood counts (CBC) in patients taking REVLIMID for MCL weekly for the first cycle (28 days), every 2 weeks during cycles 2-4, and then monthly thereafter. Patients may require dose interruption and/or dose reduction. In the MCL trial, Grade 3 or 4 neutropenia was reported in 43% of the patients. Grade 3 or 4 thrombocytopenia was reported in 28% of the patients.

Monitor complete blood counts (CBC) in patients taking REVLIMID for FL or MZL weekly for the first 3 weeks of Cycle 1 (28 days), every 2 weeks during Cycles 2-4, and then monthly thereafter. Patients may require dose interruption and/or dose reduction. In the AUGMENT and MAGNIFY trials, Grade 3 or 4 neutropenia was reported in 50% and 33%, respectively, of patients in the REVLIMID/rituximab arm. Grade 3 or 4 thrombocytopenia was reported in 2% and 8%, respectively, of patients in the REVLIMID/rituximab arm [see Adverse Reactions (6.1)].

5.4 Venous and Arterial Thromboembolism

Venous thromboembolic events (VTE [DVT and PE]) and arterial thromboembolic events (ATE, myocardial infarction and stroke) are increased in patients treated with REVLIMID.

A significantly increased risk of DVT (7.4%) and of PE (3.7%) occurred in patients with MM after at least one prior therapy who were treated with REVLIMID and dexamethasone therapy compared to patients treated in the placebo and dexamethasone group (3.1% and 0.9%) in clinical trials with varying use of anticoagulant therapies. In the newly diagnosed multiple myeloma (NDMM) study in which nearly all patients received antithrombotic prophylaxis, DVT was reported as a serious adverse reaction (3.6%, 2.0%, and 1.7%) in the Rd Continuous, Rd18, and MPT Arms, respectively. The frequency of serious adverse reactions of PE was similar between the Rd Continuous, Rd18, and MPT Arms (3.8%, 2.8%, and 3.7%, respectively) [see Boxed Warning and Adverse Reactions (6.1)].

Myocardial infarction (1.7%) and stroke (CVA) (2.3%) are increased in patients with MM after at least one prior therapy who were treated with REVLIMID and dexamethasone therapy compared to patients treated with placebo and dexamethasone (0.6%, and 0.9%) in clinical trials. In the NDMM study, myocardial infarction (including acute) was reported as a serious adverse reaction (2.3%, 0.6%, and 1.1%) in the Rd Continuous, Rd18, and MPT Arms, respectively. The frequency of serious adverse reactions of CVA was similar between the Rd Continuous, Rd18, and MPT Arms (0.8%, 0.6 %, and 0.6%, respectively) [see Adverse Reactions (6.1)].

Patients with known risk factors, including prior thrombosis, may be at greater risk and actions should be taken to try to minimize all modifiable factors (e.g. hyperlipidemia, hypertension, smoking).

In controlled clinical trials that did not use concomitant thromboprophylaxis, 21.5% overall thrombotic events (Standardized MedDRA Query Embolic and Thrombotic events) occurred in patients with refractory and relapsed MM who were treated with REVLIMID and dexamethasone compared to 8.3% thrombosis in patients treated with placebo and dexamethasone. The median time to first thrombosis event was 2.8 months. In the NDMM study in which nearly all patients received antithrombotic prophylaxis, the overall frequency of thrombotic events was 17.4% in patients in the combined Rd Continuous and Rd18 Arms, and was 11.6% in the MPT Arm. The median time to first thrombosis event was 4.3 months in the combined Rd Continuous and Rd18 Arms.

In the AUGMENT trial, the incidence of VTE (including DVT and PE) in FL or MZL patients was 3.4% in the REVLIMID/rituximab arm [see Adverse Reactions (6.1)]. In the AUGMENT trial, the incidence of ATE (including MI) in FL or MZL patients was 0.6% in the REVLIMID/rituximab arm [see Adverse Reactions (6.1)].

Thromboprophylaxis is recommended. The regimen of thromboprophylaxis should be based on an assessment of the patient's underlying risks. Instruct patients to report immediately any signs and symptoms suggestive of thrombotic events. ESAs and estrogens may further increase the risk of thrombosis and their use should be based on a benefit-risk decision in patients receiving REVLIMID [see Drug Interactions (7.2)].

5.5 Increased Mortality in Patients with CLL

In a prospective randomized (1:1) clinical trial in the first line treatment of patients with chronic lymphocytic leukemia, single agent REVLIMID therapy increased the risk of death as compared to single agent chlorambucil. In an interim analysis, there were 34 deaths among 210 patients on the REVLIMID treatment arm compared to 18 deaths among 211 patients in the chlorambucil treatment arm, and hazard ratio for overall survival was 1.92 [95% CI: 1.08 – 3.41], consistent with a 92% increase in the risk of death. The trial was halted for safety in July 2013.

Serious adverse cardiovascular reactions, including atrial fibrillation, myocardial infarction, and cardiac failure occurred more frequently in the REVLIMID treatment arm. REVLIMID is not indicated and not recommended for use in CLL outside of controlled clinical trials.

5.6 Second Primary Malignancies

In clinical trials in patients with MM receiving REVLIMID, an increase of hematologic plus solid tumor second primary malignancies (SPM) notably AML and MDS have been observed. An increase in hematologic SPM including AML and MDS occurred in 5.3% of patients with NDMM receiving REVLIMID in combination with oral melphalan compared with 1.3% of patients receiving melphalan without REVLIMID. The frequency of AML and MDS cases in patients with NDMM treated with REVLIMID in combination with dexamethasone without melphalan was 0.4%.

In patients receiving REVLIMID maintenance therapy following high dose intravenous melphalan and auto-HSCT, hematologic SPM occurred in 7.5% of patients compared to 3.3% in patients receiving placebo. The incidence of hematologic plus solid tumor (excluding squamous cell carcinoma and basal cell carcinoma) SPM was 14.9%, compared to 8.8% in patients receiving placebo with a median follow-up of 91.5 months. Non-melanoma skin cancer SPM, including squamous cell carcinoma and basal cell carcinoma, occurred in 3.9% of patients receiving REVLIMID maintenance, compared to 2.6% in the placebo arm.

In patients with relapsed or refractory MM treated with REVLIMID/dexamethasone, the incidence of hematologic plus solid tumor (excluding squamous cell carcinoma and basal cell carcinoma) SPM was 2.3% versus 0.6% in the dexamethasone alone arm. Non-melanoma skin cancer SPM, including squamous cell carcinoma and basal cell carcinoma, occurred in 3.1% of patients receiving REVLIMID/dexamethasone, compared to 0.6% in the dexamethasone alone arm.

Patients who received REVLIMID-containing therapy until disease progression did not show a higher incidence of invasive SPM than patients treated in the fixed duration REVLIMID-containing arms. Monitor patients for the development of second primary malignancies. Take into account both the potential benefit of REVLIMID and the risk of second primary malignancies when considering treatment with REVLIMID.

In the AUGMENT trial with FL or MZL patients receiving REVLIMID/rituximab therapy, hematologic plus solid tumor SPMs, notably AML, have been observed. In the AUGMENT trial, hematologic SPM of AML occurred in 0.6% of patients with FL or MZL receiving REVLIMID/rituximab therapy. The incidence of hematologic plus solid tumor SPMs (excluding nonmelanoma skin cancers) was 1.7% in the REVLIMID/rituximab arm with a median follow-up of 29.8 months (range 0.5 to 51.3 months) [see Adverse Reactions (6.1)]. Monitor patients for the development of second primary malignancies. Take into account both the potential benefit of REVLIMID and the risk of second primary malignancies when considering treatment with REVLIMID.

5.7 Increased Mortality in Patients with MM When Pembrolizumab Is Added to a Thalidomide Analogue and Dexamethasone

In two randomized clinical trials in patients with MM, the addition of pembrolizumab to a thalidomide analogue plus dexamethasone, a use for which no PD-1 or PD-L1 blocking antibody is indicated, resulted in increased mortality. Treatment of patients with MM with a PD-1 or PD-L1 blocking antibody in combination with a thalidomide analogue plus dexamethasone is not recommended outside of controlled clinical trials.

5.8 Hepatotoxicity

Hepatic failure, including fatal cases, has occurred in patients treated with REVLIMID in combination with dexamethasone. In clinical trials, 15% of patients experienced hepatotoxicity (with hepatocellular, cholestatic and mixed characteristics); 2% of patients with MM and 1% of patients with myelodysplasia had serious hepatotoxicity events. The mechanism of drug-induced hepatotoxicity is unknown. Pre-existing viral liver disease, elevated baseline liver enzymes, and concomitant medications may be risk factors. Monitor liver enzymes periodically. Stop REVLIMID upon elevation of liver enzymes. After return to baseline values, treatment at a lower dose may be considered.

5.9 Severe Cutaneous Reactions

Severe cutaneous reactions including Stevens-Johnson syndrome (SJS), toxic epidermal necrolysis (TEN), and drug reaction with eosinophilia and systemic symptoms (DRESS) have been reported. DRESS may present with a cutaneous reaction (such as rash or exfoliative dermatitis), eosinophilia, fever, and/or lymphadenopathy with systemic complications such as hepatitis, nephritis, pneumonitis, myocarditis, and/or pericarditis. These events can be fatal. Patients with a prior history of Grade 4 rash associated with thalidomide treatment should not receive REVLIMID. Consider REVLIMID interruption or discontinuation for Grade 2-3 skin rash. Permanently discontinue REVLIMID for Grade 4 rash, exfoliative or bullous rash, or for other severe cutaneous reactions such as SJS, TEN or DRESS [see Dosage and Administration (2.5)].

5.10 Tumor Lysis Syndrome

Fatal instances of tumor lysis syndrome (TLS) have been reported during treatment with REVLIMID. The patients at risk of TLS are those with high tumor burden prior to treatment. Monitor patients at risk closely and take appropriate preventive approaches. In the AUGMENT trial in FL or MZL patients, TLS occurred in 2 patients (1.1%) in the REVLIMID/rituximab arm. TLS occurred in 1 patient (0.5%) in the MAGNIFY trial during the REVLIMID/rituximab induction period; the event was a serious, Grade 3 adverse reaction.

5.11 Tumor Flare Reaction

Tumor flare reaction (TFR), including fatal reactions, have occurred during investigational use of REVLIMID for CLL and lymphoma, and is characterized by tender lymph node swelling, low grade fever, pain and rash. REVLIMID is not indicated and not recommended for use in CLL outside of controlled clinical trials.

Monitoring and evaluation for TFR is recommended in patients with MCL, FL, or MZL. Tumor flare reaction may mimic progression of disease (PD).

In the MCL trial, 13/134 (10%) of subjects experienced TFR; all reports were Grade 1 or 2 in severity. All of the events occurred in Cycle 1 and one patient developed TFR again in Cycle 11. In the AUGMENT trial in FL or MZL patients, TFR was reported in 19/176 (10.8%) of patients in REVLIMID with rituximab arm; one patient in the REVLIMID/rituximab arm experienced a Grade 3 TFR. In the MAGNIFY trial, 9/222 (4.1%) of patients experienced TFR; all reports were Grade 1 or 2 in severity and 1 event was considered as serious. In a separate MCL phase 2 trial, one case of TFR resulted in a fatal outcome.

REVLIMID may be continued in patients with Grade 1 and 2 TFR without interruption or modification, at the physician's discretion. Patients with Grade 1 and 2 TFR may also be treated with corticosteroids, non-steroidal anti-inflammatory drugs (NSAIDs) and/or narcotic analgesics for management of TFR symptoms. In patients with Grade 3 or 4 TFR, it is recommended to withhold treatment with REVLIMID until TFR resolves to ≤ Grade 1. Patients with Grade 3 or 4 TFR may be treated for management of symptoms per the guidance for treatment of Grade 1 and 2 TFR.

5.12 Impaired Stem Cell Mobilization

A decrease in the number of CD34+ cells collected after treatment (> 4 cycles) with REVLIMID has been reported. In patients who are auto-HSCT candidates, referral to a transplant center should occur early in treatment to optimize the timing of the stem cell collection. In patients who received more than 4 cycles of a REVLIMID-containing treatment or for whom inadequate numbers of CD 34+ cells have been collected with G-CSF alone, G-CSF with cyclophosphamide or the combination of G-CSF with a CXCR4 inhibitor may be considered.

5.13 Thyroid Disorders

Both hypothyroidism and hyperthyroidism have been reported [see Adverse Reactions (6.2)]. Measure thyroid function before start of REVLIMID treatment and during therapy.

5.14 Early Mortality in Patients with MCL

In another MCL study, there was an increase in early deaths (within 20 weeks), 12.9% in the REVLIMID arm versus 7.1% in the control arm. On exploratory multivariate analysis, risk factors for early deaths include high tumor burden, MIPI score at diagnosis, and high WBC at baseline (≥ 10 x 10^9/L).

5.15 Hypersensitivity

Hypersensitivity, including angioedema, anaphylaxis, and anaphylactic reactions to REVLIMID has been reported. Permanently discontinue REVLIMID for angioedema and anaphylaxis [see Dosage and Administration (2.2)].

6 ADVERSE REACTIONS

The following clinically significant adverse reactions are described in detail in other sections of the prescribing information:

- Embryo-Fetal Toxicity [see Boxed Warning, Warnings and Precautions (5.1, 5.2)]
- Hematologic Toxicity [see Boxed Warning, Warnings and Precautions (5.3)]
- Venous and Arterial Thromboembolism [see Boxed Warning, Warnings and Precautions (5.4)]
- Increased Mortality in Patients with CLL [see Warnings and Precautions (5.5)]
- Second Primary Malignancies [see Warnings and Precautions (5.6)]
- Increased Mortality in Patients with MM When Pembrolizumab Is Added to a Thalidomide Analogue and Dexamethasone [see Warnings and Precautions (5.7)]
- Hepatotoxicity [see Warnings and Precautions (5.8)]
- Severe Cutaneous Reactions[see Warnings and Precautions (5.9)]
- Tumor Lysis Syndrome [see Warnings and Precautions (5.10)]
- Tumor Flare Reactions [see Warnings and Precautions (5.11)]
- Impaired Stem Cell Mobilization [see Warnings and Precautions (5.12)]
- Thyroid Disorders [see Warnings and Precautions (5.13)]
- Early Mortality in Patients with MCL [see Warnings and Precautions (5.14)]
- Hypersensitivity [see Warnings and Precautions (5.15)]

6.1 Clinical Trials Experience

Because clinical trials are conducted under widely varying conditions, adverse reaction rates observed in the clinical trials of a drug cannot be directly compared to rates in the clinical trials of another drug and may not reflect the rates observed in practice.

Newly Diagnosed MM – REVLIMID Combination Therapy:

Data were evaluated from 1613 patients in a large phase 3 study who received at least one dose of REVLIMID with low dose dexamethasone (Rd) given for 2 different durations of time (i.e., until progressive disease [Arm Rd Continuous; N=532] or for up to eighteen 28-day cycles [72 weeks, Arm Rd18; N=540] or who received melphalan, prednisone and thalidomide (Arm MPT; N=541) for a maximum of twelve 42-day cycles (72 weeks). The median treatment duration in the Rd Continuous arm was 80.2 weeks (range 0.7 to 246.7) or 18.4 months (range 0.16 to 56.7).

In general, the most frequently reported adverse reactions were comparable in Arm Rd Continuous and Arm Rd18, and included diarrhea, anemia, constipation, peripheral edema, neutropenia, fatigue, back pain, nausea, asthenia, and insomnia. The most frequently reported Grade 3 or 4 reactions included neutropenia, anemia, thrombocytopenia, pneumonia, asthenia, fatigue, back pain, hypokalemia, rash, cataract, lymphopenia, dyspnea, DVT, hyperglycemia, and leukopenia. The highest frequency of infections occurred in Arm Rd Continuous (75%) compared to Arm MPT (56%). There were more grade 3 and 4 and serious adverse reactions of infection in Arm Rd Continuous than either Arm MPT or Rd18.

In the Rd Continuous arm, the most common adverse reactions leading to dose interruption of REVLIMID were infection events (28.8%); overall, the median time to the first dose interruption of REVLIMID was 7 weeks. The most common adverse reactions leading to dose reduction of REVLIMID in the Rd Continuous arm were hematologic events (10.7%); overall, the median time to the first dose reduction of REVLIMID was 16 weeks. In the Rd Continuous arm, the most common adverse reactions leading to discontinuation of REVLIMID were infection events (3.4%).

In both Rd arms, the frequencies of onset of adverse reactions were generally highest in the first 6 months of treatment and then the frequencies decreased over time or remained stable throughout treatment, except for cataracts. The frequency of onset of cataracts increased over time with 0.7% during the first 6 months and up to 9.6% by the 2nd year of treatment with Rd Continuous.

Table 4 summarizes the adverse reactions reported for the Rd Continuous, Rd18, and MPT treatment arms.

Table 4: All Adverse Reactions in ≥5% and Grade 3/4 Adverse Reactions in ≥1% of Patients with MM in the Rd Continuous or Rd18 Arms*
Body System Adverse Reaction | All Adverse Reactionsa |  |  | Grade 3/4 Adverse Reactionsb
Body System Adverse Reaction | Rd Continuous (N = 532) | Rd18 (N = 540) | MPT (N = 541) | Rd Continuous (N = 532) | Rd18 (N = 540) | MPT (N = 541)
General disorders and administration site conditions
Fatigue% | 173 (33) | 177 (33) | 154 (28) | 39 (7) | 46 (9) | 31 (6)
Asthenia | 150 (28) | 123 (23) | 124 (23) | 41 (8) | 33 (6) | 32 (6)
Pyrexiac | 114 (21) | 102 (19) | 76 (14) | 13 (2) | 7 (1) | 7 (1)
Non-cardiac chest pain f | 29 (5) | 31 (6) | 18 (3) | <1% | < 1% | < 1%
Gastrointestinal disorders
Diarrhea | 242 (45) | 208 (39) | 89 (16) | 21 (4) | 18 (3) | 8 (1)
Abdominal pain% f | 109 (20) | 78 (14) | 60 (11) | 7 (1) | 9 (2) | < 1%
Dyspepsia f | 57 (11) | 28 (5) | 36 (7) | <1% | < 1% | 0 (0)
Musculoskeletal and connective tissue disorders
Back painc | 170 (32) | 145 (27) | 116 (21) | 37 (7) | 34 (6) | 28 (5)
Muscle spasms f | 109 (20) | 102 (19) | 61 (11) | < 1% | < 1% | < 1%
Arthralgia f | 101 (19) | 71 (13) | 66 (12) | 9 (2) | 8 (1) | 8 (1)
Bone pain f | 87 (16) | 77 (14) | 62 (11) | 16 (3) | 15 (3) | 14 (3)
Pain in extremity f | 79 (15) | 66 (12) | 61 (11) | 8 (2) | 8 (1) | 7 (1)
Musculoskeletal pain f | 67 (13) | 59 (11) | 36 (7) | < 1% | < 1% | < 1%
Musculoskeletal chest pain f | 60 (11) | 51 (9) | 39 (7) | 6 (1) | < 1% | < 1%
Muscular weakness f | 43 (8) | 35 (6) | 29 (5) | < 1% | 8 (1) | < 1%
Neck pain f | 40 (8) | 19 (4) | 10 (2) | < 1% | < 1% | < 1%
Infections and infestations
Bronchitisc | 90 (17) | 59 (11) | 43 (8) | 9 (2) | 6 (1) | < 1%
Nasopharyngitis f | 80 (15) | 54 (10) | 33 (6) | 0 (0) | 0 (0) | 0 (0)
Urinary tract infection f | 76 (14) | 63 (12) | 41 (8) | 8 (2) | 8 (1) | < 1%
Upper respiratory tract infectionc% f | 69 (13) | 53 (10) | 31 (6) | < 1% | 8 (1) | < 1%
Pneumoniac@ | 93 (17) | 87 (16) | 56 (10) | 60 (11) | 57 (11) | 41 (8)
Respiratory tract infection% | 35 (7) | 25 (5) | 21 (4) | 7 (1) | < 1% | < 1%
Influenza f | 33 (6) | 23 (4) | 15 (3) | < 1% | < 1% | 0 (0)
Gastroenteritis f | 32 (6) | 17 (3) | 13 (2) | 0 (0) | < 1% | < 1%
Lower respiratory tract infection | 29 (5) | 14 (3) | 16 (3) | 10 (2) | < 1% | < 1%
Rhinitis f | 29 (5) | 24 (4) | 14 (3) | 0 (0) | 0 (0) | 0 (0)
Cellulitisc | < 5% | < 5% | < 5% | 8 (2) | < 1% | < 1%
Sepsisc@ | 33 (6) | 26 (5) | 18 (3) | 26 (5) | 20 (4) | 13 (2)
Nervous system disorders
Headache f | 75 (14) | 52 (10) | 56 (10) | < 1% | < 1% | < 1%
Dysgeusia f | 39 (7) | 45 (8) | 22 (4) | < 1% | 0 (0.0) | < 1%
Blood and lymphatic system disordersd
Anemia | 233 (44) | 193 (36) | 229 (42) | 97 (18) | 85 (16) | 102 (19)
Neutropenia | 186 (35) | 178 (33) | 328 (61) | 148 (28) | 143 (26) | 243 (45)
Thrombocytopenia | 104 (20) | 100 (19) | 135 (25) | 44 (8) | 43 (8) | 60 (11)
Febrile neutropenia | 7 (1) | 17 (3) | 15 (3) | 6 (1) | 16 (3) | 14 (3)
Pancytopenia | < 1% | 6 (1) | 7 (1) | < 1% | < 1% | < 1%
Respiratory, thoracic and mediastinal disorders
Cough f | 121 (23) | 94 (17) | 68 (13) | < 1% | < 1% | < 1%
Dyspneac,e | 117 (22) | 89 (16) | 113 (21) | 30 (6) | 22 (4) | 18 (3)
Epistaxis f | 32 (6) | 31 (6) | 17 (3) | < 1% | < 1% | 0 (0)
Oropharyngeal pain f | 30 (6) | 22 (4) | 14 (3) | 0 (0) | 0 (0) | 0 (0)
Dyspnea exertional e | 27 (5) | 29 (5) | < 5% | 6 (1) | < 1% | 0 (0)
Metabolism and nutrition disorders
Decreased appetite | 123 (23) | 115 (21) | 72 (13) | 14 (3) | 7 (1) | < 1%
Hypokalemia% | 91 (17) | 62 (11) | 38 (7) | 35 (7) | 20 (4) | 11 (2)
Hyperglycemia | 62 (12) | 52 (10) | 19 (4) | 28 (5) | 23 (4) | 9 (2)
Hypocalcemia | 57 (11) | 56 (10) | 31 (6) | 23 (4) | 19 (4) | 8 (1)
Dehydration% | 25 (5) | 29 (5) | 17 (3) | 8 (2) | 13 (2) | 9 (2)
Gout e | < 5% | < 5% | < 5% | 8 (2) | 0 (0) | 0 (0)
Diabetes mellitus% e | < 5% | < 5% | < 5% | 8 (2) | < 1% | < 1%
Hypophosphatemia e | < 5% | < 5% | < 5% | 7 (1) | < 1% | < 1%
Hyponatremia% e | < 5% | < 5% | < 5% | 7 (1) | 13 (2) | 6 (1)
Skin and subcutaneous tissue disorders
Rash | 139 (26) | 151 (28) | 105 (19) | 39 (7) | 38 (7) | 33 (6)
Pruritus f | 47 (9) | 49 (9) | 24 (4) | < 1% | < 1% | < 1%
Psychiatric disorders
Insomnia | 147 (28) | 127 (24) | 53 (10) | < 1% | 6 (1) | 0 (0)
Depression | 58 (11) | 46 (9) | 30 (6) | 10 (2) | < 1% | < 1%
Vascular disorders
Deep vein thrombosisc% | 55 (10) | 39 (7) | 22 (4) | 30 (6) | 20 (4) | 15 (3)
Hypotensionc% | 51 (10) | 35 (6) | 36 (7) | 11 (2) | 8 (1) | 6 (1)
Injury, Poisoning, and Procedural Complications
Fall f | 43 (8) | 25 (5) | 25 (5) | < 1% | 6 (1) | 6 (1)
Contusion f | 33 (6) | 24 (4) | 15 (3) | < 1% | < 1% | 0 (0)
Eye disorders
Cataract | 73 (14) | 31 (6) | < 1% | 31 (6) | 14 (3) | < 1%
Cataract subcapsular e | < 5% | < 5% | < 5% | 7 (1) | 0 (0) | 0 (0)
Investigations
Weight decreased | 72 (14) | 78 (14) | 48 (9) | 11 (2) | < 1% | < 1%
Cardiac disorders
Atrial fibrillationc | 37 (7) | 25 (5) | 25 (5) | 13 (2) | 9 (2) | 6 (1)
Myocardial infarction (including acute)c ,e | < 5% | < 5% | < 5% | 10 (2) | < 1% | < 1%
Renal and Urinary disorders
Renal failure (including acute)c@,f | 49 (9) | 54 (10) | 37 (7) | 28 (5) | 33 (6) | 29 (5)
Neoplasms benign, malignant and unspecified (Including cysts and polyps)
Squamous cell carcinomac e | < 5% | < 5% | < 5% | 8 (2) | < 1% | 0 (0)
Basal cell carcinomac e,f | < 5% | < 5% | < 5% | < 1% | < 1% | 0 (0)
Note: A subject with multiple occurrences of an adverse reaction is counted only once under the applicable Body System/Adverse Reaction.
a All treatment-emergent adverse events in at least 5% of subjects in the Rd Continuous or Rd18 Arms and at least a 2% higher frequency (%) in either the Rd Continuous or Rd18 Arms compared to the MPT Arm.
b All grade 3 or 4 treatment-emergent adverse events in at least 1% of subjects in the Rd Continuous or Rd18 Arms and at least a 1% higher frequency (%) in either the Rd Continuous or Rd18 Arms compared to the MPT Arm.
c Serious treatment-emergent adverse events in at least 1% of subjects in the Rd Continuous or Rd18 Arms and at least a 1% higher frequency (%) in either the Rd Continuous or Rd18 Arms compared to the MPT Arm.
d Preferred terms for the blood and lymphatic system disorders body system were included by medical judgment as known adverse reactions for Rd Continuous/Rd18, and have also been reported as serious.
e Footnote “a” not applicable.
f Footnote “b” not applicable.
@ - adverse reactions in which at least one resulted in a fatal outcome.
% - adverse reactions in which at least one was considered to be life threatening (if the outcome of the reaction was death, it is included with death cases).
*Adverse reactions included in combined adverse reaction terms:
Abdominal Pain: Abdominal pain, abdominal pain upper, abdominal pain lower, gastrointestinal pain
Pneumonias: Pneumonia, lobar pneumonia, pneumonia pneumococcal, bronchopneumonia, pneumocystis jiroveci pneumonia, pneumonia legionella, pneumonia staphylococcal, pneumonia klebsiella, atypical pneumonia, pneumonia bacterial, pneumonia escherichia, pneumonia streptococcal, pneumonia viral
Sepsis: Sepsis, septic shock, urosepsis, escherichia sepsis, neutropenic sepsis, pneumococcal sepsis, staphylococcal sepsis, bacterial sepsis, meningococcal sepsis, enterococcal sepsis, klebsiella sepsis, pseudomonal sepsis
Rash: Rash, rash pruritic, rash erythematous, rash maculo-papular, rash generalized, rash papular, exfoliative rash, rash follicular, rash macular, drug rash with eosinophilia and systemic symptoms, erythema multiforme, rash pustular
Deep Vein Thrombosis: Deep vein thrombosis, venous thrombosis limb, venous thrombosis

Newly Diagnosed MM - REVLIMID Maintenance Therapy Following Auto-HSCT:

Data were evaluated from 1018 patients in two randomized trials who received at least one dose of REVLIMID 10 mg daily as maintenance therapy after auto-HSCT until progressive disease or unacceptable toxicity. The mean treatment duration for REVLIMID treatment was 30.3 months for Maintenance Study 1 and 24.0 months for Maintenance Study 2 (overall range across both studies from 0.1 to 108 months). As of the cut-off date of 1 Mar 2015, 48 patients (21%) in the Maintenance Study 1 REVLIMID arm were still on treatment and none of the patients in the Maintenance Study 2 REVLIMID arm were still on treatment at the same cut-off date

The adverse reactions listed from Maintenance Study 1 included events reported post-transplant (completion of high-dose melphalan /auto-HSCT), and the maintenance treatment period. In Maintenance Study 2, the adverse reactions were from the maintenance treatment period only. In general, the most frequently reported adverse reactions (more than 20% in the REVLIMID arm) across both studies were neutropenia, thrombocytopenia, leukopenia, anemia, upper respiratory tract infection, bronchitis, nasopharyngitis, cough, gastroenteritis, diarrhea, rash, fatigue, asthenia, muscle spasm and pyrexia. The most frequently reported Grade 3 or 4 reactions (more than 20% in the REVLIMID arm) included neutropenia, thrombocytopenia, and leukopenia. The serious adverse reactions lung infection and neutropenia (more than 4.5%) occurred in the REVLIMID arm.

For REVLIMID, the most common adverse reactions leading to dose interruption were hematologic events (29.7%, data available in Maintenance Study 2 only). The most common adverse reaction leading to dose reduction of REVLIMID were hematologic events (17.7%, data available in Maintenance Study 2 only). The most common adverse reactions leading to discontinuation of REVLIMID were thrombocytopenia (2.7%) in Maintenance Study 1 and neutropenia (2.4%) in Maintenance Study 2.

The frequencies of onset of adverse reactions were generally highest in the first 6 months of treatment and then the frequencies decreased over time or remained stable throughout treatment.

Table 5 summarizes the adverse reactions reported for the REVLIMID and placebo maintenance treatment arms.

Table 5: All Adverse Reactions in ≥5% and Grade 3/4 Adverse Reactions in ≥1% of Patients with MM in the REVLIMID Vs Placebo Arms*
Body System Adverse Reaction | Maintenance Study 1 |  |  |  | Maintenance Study 2
Body System Adverse Reaction | All Adverse Reactions a |  | Grade 3/4 Adverse Reactions b |  | All Adverse Reactions a |  | Grade 3/4 Adverse Reactions b
Body System Adverse Reaction | REVLIMID (N=224) n (%) | Placebo (N=221) n (%) | REVLIMID (N=224) n (%) | Placebo (N=221) n (%) | REVLIMID (N=293) n (%) | Placebo (N=280) n (%) | REVLIMID (N=293) n (%) | Placebo (N=280) n (%)
Blood and lymphatic system disorders
Neutropenia c % | 177 (79) | 94 (43) | 133 (59) | 73 (33) | 178 (61) | 33 (12) | 158 (54) | 21 (8)
Thrombocytopenia c % | 162 (72) | 101 (46) | 84 (38) | 67 (30) | 69 (24) | 29 (10) | 38 (13) | 8 (3)
Leukopenia c | 51 (23) | 25 (11) | 45 (20) | 22 (10) | 93 (32) | 21 (8) | 71 (24) | 5 (2)
Anemia | 47 (21) | 27 (12) | 23 (10) | 18 (8) | 26 (9) | 15 (5) | 11 (4) | 3 (1)
Lymphopenia | 40 (18) | 29 (13) | 37 (17) | 26 (12) | 13 (4) | 3 (1) | 11 (4) | < 1%
Pancytopenia c d % | < 1% | 0 (0) | 0 (0) | 0 (0) | 12 (4) | < 1% | 7 (2) | < 1%
Febrile neutropenia c | 39 (17) | 34 (15) | 39 (17) | 34 (15) | 7 (2) | < 1% | 5 (2) | < 1%
Infections and infestations#
Upper respiratory tract infection e | 60 (27) | 35 (16) | 7 (3) | 9 (4) | 32 (11) | 18 (6) | < 1% | 0 (0)
Neutropenic infection | 40 (18) | 19 (9) | 27 (12) | 14 (6) | 0 (0) | 0 (0) | 0 (0) | 0 (0)
Pneumonias* c % | 31 (14) | 15 (7) | 23 (10) | 7 (3) | 50 (17) | 13 (5) | 27 (9) | 5 (2)
Bronchitis c | 10 (4) | 9 (4) | < 1% | 5 (2) | 139 (47) | 104 (37) | 4 (1) | < 1%
Nasopharyngitis e | 5 (2) | < 1% | 0 (0) | 0 (0) | 102 (35) | 84 (30) | < 1% | 0 (0)
Gastroenteritis c | 0 (0) | 0 (0) | 0 (0) | 0 (0) | 66 (23) | 55 (20) | 6 (2) | 0 (0)
Rhinitis e | < 1% | 0 (0) | 0 (0) | 0 (0) | 44 (15) | 19 (7) | 0 (0) | 0 (0)
Sinusitis e | 8 (4) | 3 (1) | 0 (0) | 0 (0) | 41 (14) | 26 (9) | 0 (0) | < 1%
Influenza c | 8 (4) | 5 (2) | < 1% | < 1% | 39 (13) | 19 (7) | 3 (1) | 0 (0)
Lung infection c | 21 (9) | < 1% | 19 (8) | < 1% | 9 (3) | 4 (1) | < 1% | 0 (0)
Lower respiratory tract infection e | 13 (6) | 5 (2) | 6 (3) | 4 (2) | 4 (1) | 4 (1) | 0 (0) | < 1%
Infection c | 12 (5) | 6 (3) | 9 (4) | 5 (2) | 17 (6) | 5 (2) | 0 (0) | 0 (0)
Urinary tract infection c d e | 9 (4) | 5 (2) | 4 (2) | 4 (2) | 22 (8) | 17 (6) | < 1% | 0 (0)
Lower respiratory tract infection bacterial d | 6 (3) | < 1% | 4 (2) | 0 (0) | 0 (0) | 0 (0) | 0 (0) | 0 (0)
Bacteremia d | 5 (2) | 0 (0) | 4 (2) | 0 (0) | 0 (0) | 0 (0) | 0 (0) | 0 (0)
Herpes zoster c d | 11 (5) | 10 (5) | 3 (1) | < 1% | 29 (10) | 25 (9) | 6 (2) | < 1%
Sepsis* c d @ | < 1% | < 1% | 0 (0) | 0 (0) | 6 (2) | < 1% | 4 (1) | < 1%
Gastrointestinal disorders
Diarrhea | 122 (54) | 83 (38) | 22 (10) | 17 (8) | 114 (39) | 34 (12) | 7 (2) | 0 (0)
Nausea e | 33 (15) | 22 (10) | 16 (7) | 10 (5) | 31 (11) | 28 (10) | 0 (0) | 0 (0)
Vomiting | 17 (8) | 12 (5) | 8 (4) | 5 (2) | 16 (5) | 15 (5) | < 1% | 0 (0)
Constipation e | 12 (5) | 8 (4) | 0 (0) | 0 (0) | 37 (13) | 25 (9) | < 1% | 0 (0)
Abdominal pain e | 8 (4) | 7 (3) | < 1% | 4 (2) | 31 (11) | 15 (5) | < 1% | < 1%
Abdominal pain upper e | 0 (0) | 0 (0) | 0 (0) | 0 (0) | 20 (7) | 12 (4) | < 1% | 0 (0)
General disorders and administration site conditions
Asthenia | 0 (0) | < 1% | 0 (0) | 0 (0) | 87 (30) | 53 (19) | 10 (3) | < 1%
Fatigue | 51 (23) | 30 (14) | 21 (9) | 9 (4) | 31 (11) | 15 (5) | 3 (1) | 0 (0)
Pyrexia e | 17 (8) | 10 (5) | < 1% | < 1% | 60 (20) | 26 (9) | < 1% | 0 (0)
Skin and subcutaneous tissue disorders
Dry skin e | 9 (4) | 4 (2) | 0 (0) | 0 (0) | 31 (11) | 21 (8) | 0 (0) | 0 (0)
Rash | 71 (32) | 48 (22) | 11 (5) | 5 (2) | 22 (8) | 17 (6) | 3 (1) | 0 (0)
Pruritus | 9 (4) | 4 (2) | 3 (1) | 0 (0) | 21 (7) | 25 (9) | < 1% | 0 (0)
Nervous system disorders
Paresthesia e | < 1% | 0 (0) | 0 (0) | 0 (0) | 39 (13) | 30 (11) | < 1% | 0 (0)
Peripheral neuropathy* e | 34 (15) | 30 (14) | 8 (4) | 8 (4) | 29 (10) | 15 (5) | 4 (1) | < 1%
Headache d | 11 (5) | 8 (4) | 5 (2) | < 1% | 25 (9) | 21 (8) | 0 (0) | 0 (0)
Investigations
Alanine aminotransferase increased | 16 (7) | 3 (1) | 8 (4) | 0 (0) | 5 (2) | 5 (2) | 0 (0) | < 1%
Aspartate aminotransferase increased d | 13 (6) | 5 (2) | 6 (3) | 0 (0) | < 1% | 5 (2) | 0 (0) | 0 (0)
Metabolism and nutrition disorders
Hypokalemia | 24 (11) | 13 (6) | 16 (7) | 12 (5) | 12 (4) | < 1% | < 1% | 0 (0)
Dehydration | 9 (4) | 5 (2) | 7 (3) | 3 (1) | 0 (0) | 0 (0) | 0 (0) | 0 (0)
Hypophosphatemia d | 16 (7) | 15 (7) | 13 (6) | 14 (6) | 0 (0) | < 1% | 0 (0) | 0 (0)
Musculoskeletal and connective tissue disorders
Muscle spasms e | 0 (0) | < 1% | 0 (0) | 0 (0) | 98 (33) | 43 (15) | < 1% | 0 (0)
Myalgia e | 7 (3) | 8 (4) | 3 (1) | 5 (2) | 19 (6) | 12 (4) | < 1% | < 1%
Musculoskeletal pain e | < 1% | < 1% | 0 (0) | 0 (0) | 19 (6) | 11 (44) | 0 (0) | 0 (0)
Hepatobiliary disorders
Hyperbilirubinemia e | 34 (15) | 19 (9) | 4 (2) | < 1% | 4 (1) | < 1% | < 1% | 0 (0)
Respiratory, thoracic and mediastinal disorders
Cough e | 23 (10) | 12 (5) | 3 (1) | < 1% | 80 (27) | 56 (20) | 0 (0) | 0 (0)
Dyspnea c e | 15 (7) | 9 (4) | 8 (4) | 4 (2) | 17 (6) | 9 (3) | < 1% | 0 (0)
Rhinorrhea e | 0 (0) | 3 (1) | 0 (0) | 0 (0) | 15 (5) | 6 (2) | 0 (0) | 0 (0)
Pulmonary embolism c d e | 0 (0) | 0 (0) | 0 (0) | 0 (0) | 3 (1) | 0 (0) | < 1% | 0 (0)
Vascular disorders
Deep vein thrombosis*c d % | 8 (4) | < 1% | 5 (2) | < 1% | 7 (2) | < 1% | 4 (1) | < 1%
Neoplasms benign, malignant and unspecified (including cysts and polyps)
Myelodysplastic syndrome c d e | 5 (2) | 0 (0) | < 1% | 0 (0) | 3 (1) | 0 (0) | < 1% | 0 (0)
Note: Adverse Events (AEs) are coded to Body System /Adverse Reaction using MedDRA v15.1. A subject with multiple occurrences of an adverse reaction is counted only once under the applicable Body System/Adverse Reaction.
a All treatment-emergent AEs in at least 5% of patients in the REVLIMID Maintenance group and at least 2% higher frequency (%) than the Placebo Maintenance group.
b All grade 3 or 4 treatment-emergent AEs in at least 1% of patients in the REVLIMID Maintenance group and at least 1% higher frequency (%) than the Placebo Maintenance group.
c All serious treatment-emergent AEs in at least 1% of patients in the REVLIMID Maintenance group and at least 1% higher frequency (%) than the Placebo Maintenance group.
d Footnote “a” not applicable for either study
e Footnote “b” not applicable for either study
@ - ADRs where at least one resulted in a fatal outcome
% - ADRs where at least one was considered to be Life Threatening (if the outcome of the event was death, it is included with death cases)
# - All adverse reactions under Body System of Infections and Infestation except for rare infections of Public Health interest will be considered listed
*Adverse Reactions for combined ADR terms (based on relevant TEAE PTs included in Maintenance Studies 1 and 2 [per MedDRA v 15.1]):
Pneumonias Bronchopneumonia, Lobar pneumonia, Pneumocystis jiroveci pneumonia, Pneumonia, Pneumonia klebsiella, Pneumonia legionella, Pneumonia mycoplasmal, Pneumonia pneumococcal, Pneumonia streptococcal, Pneumonia viral, Lung disorder, Pneumonitis
Sepsis: Bacterial sepsis, Pneumococcal sepsis, Sepsis, Septic shock, Staphylococcal sepsis
Peripheral neuropathy: Neuropathy peripheral, Peripheral motor neuropathy, Peripheral sensory neuropathy, Polyneuropathy
Deep vein thrombosis: Deep vein thrombosis, Thrombosis, Venous thrombosis

After At Least One Prior Therapy for MM:

Data were evaluated from 703 patients in two studies who received at least one dose of REVLIMID/dexamethasone (353 patients) or placebo/dexamethasone (350 patients).

In the REVLIMID/dexamethasone treatment group, 269 patients (76%) had at least one dose interruption with or without a dose reduction of REVLIMID compared to 199 patients (57%) in the placebo/dexamethasone treatment group. Of these patients who had one dose interruption with or without a dose reduction, 50% in the REVLIMID/dexamethasone treatment group had at least one additional dose interruption with or without a dose reduction compared to 21% in the placebo/dexamethasone treatment group. Most adverse reactions and Grade 3/4 adverse reactions were more frequent in patients who received the combination of REVLIMID/dexamethasone compared to placebo/dexamethasone.

Tables 6, 7, and 8 summarize the adverse reactions reported for REVLIMID/dexamethasone and placebo/dexamethasone groups.

Table 6: Adverse Reactions Reported in ≥5% of Patients and with a ≥2% Difference in Proportion of Patients with MM between the REVLIMID/dexamethasone and Placebo/dexamethasone Groups
Body System Adverse Reaction | REVLIMID/Dex (N=353) n (%) | Placebo/Dex (N=350) n (%)
Blood and lymphatic system disorders
Neutropenia% | 149 (42) | 22 (6)
Anemia@ | 111 (31) | 83 (24)
Thrombocytopenia@ | 76 (22) | 37 (11)
Leukopenia | 28 (8) | 4 (1)
Lymphopenia | 19 (5) | 5 (1)
General disorders and administration site conditions
Fatigue | 155 (44) | 146 (42)
Pyrexia | 97 (27) | 82 (23)
Peripheral edema | 93 (26) | 74 (21)
Chest pain | 29 (8) | 20 (6)
Lethargy | 24 (7) | 8 (2)
Gastrointestinal disorders
Constipation | 143 (41) | 74 (21)
Diarrhea@ | 136 (39) | 96 (27)
Nausea@ | 92 (26) | 75 (21)
Vomiting@ | 43 (12) | 33 (9)
Abdominal pain@ | 35 (10) | 22 (6)
Dry mouth | 25 (7) | 13 (4)
Musculoskeletal and connective tissue disorders
Muscle cramp | 118 (33) | 74 (21)
Back pain | 91 (26) | 65 (19)
Bone pain | 48 (14) | 39 (11)
Pain in limb | 42 (12) | 32 (9)
Nervous system disorders
Dizziness | 82 (23) | 59 (17)
Tremor | 75 (21) | 26 (7)
Dysgeusia | 54 (15) | 34 (10)
Hypoesthesia | 36 (10) | 25 (7)
Neuropathya | 23 (7) | 13 (4)
Respiratory, thoracic and mediastinal disorders
Dyspnea | 83 (24) | 60 (17)
Nasopharyngitis | 62 (18) | 31 (9)
Pharyngitis | 48 (14) | 33 (9)
Bronchitis | 40 (11) | 30 (9)
Infectionsb and infestations
Upper respiratory tract infection | 87 (25) | 55 (16)
Pneumonia@ | 48 (14) | 29 (8)
Urinary tract infection | 30 (8) | 19 (5)
Sinusitis | 26 (7) | 16 (5)
Skin and subcutaneous system disorders
Rashc | 75 (21) | 33 (9)
Sweating increased | 35 (10) | 25 (7)
Dry skin | 33 (9) | 14 (4)
Pruritus | 27 (8) | 18 (5)
Metabolism and nutrition disorders
Anorexia | 55 (16) | 34 (10)
Hypokalemia | 48 (14) | 21 (6)
Hypocalcemia | 31 (9) | 10 (3)
Appetite decreased | 24 (7) | 14 (4)
Dehydration | 23 (7) | 15 (4)
Hypomagnesemia | 24 (7) | 10 (3)
Investigations
Weight decreased | 69 (20) | 52 (15)
Eye disorders
Blurred vision | 61 (17) | 40 (11)
Vascular disorders
Deep vein thrombosis% | 33 (9) | 15 (4)
Hypertension | 28 (8) | 20 (6)
Hypotension | 25 (7) | 15 (4)

Table 7: Grade 3/4 Adverse Reactions Reported in ≥2% Patients and with a ≥1% Difference in Proportion of Patients with MM between the REVLIMID/dexamethasone and Placebo/dexamethasone groups
Body System Adverse Reaction | REVLIMID/Dex (N=353) n (%) | Placebo/Dex (N=350) n (%)
Blood and lymphatic system disorders
Neutropenia% | 118 (33) | 12 (3)
Thrombocytopenia@ | 43 (12) | 22 (6)
Anemia@ | 35 (10) | 20 (6)
Leukopenia | 14 (4) | < 1%
Lymphopenia | 10 (3) | 4 (1)
Febrile neutropenia% | 8 (2) | 0 (0)
General disorders and administration site conditions
Fatigue | 23 (7) | 17 (5)
Vascular disorders
Deep vein thrombosis% | 29 (8) | 12 (3)
Infections and infestations
Pneumonia@ | 30 (8) | 19 (5)
Urinary tract infection | 5 (1) | < 1%
Metabolism and nutrition disorders
Hypokalemia | 17 (5) | 5 (1)
Hypocalcemia | 13 (4) | 6 (2)
Hypophosphatemia | 9 (3) | 0 (0)
Respiratory, thoracic and mediastinal disorders
Pulmonary embolism@ | 14 (4) | < 1%
Respiratory distress@ | 4 (1) | 0 (0)
Musculoskeletal and connective tissue disorders
Muscle weakness | 20 (6) | 10 (3)
Gastrointestinal disorders
Diarrhea@ | 11 (3) | 4 (1)
Constipation | 7 (2) | < 1%
Nausea@ | 6 (2) | < 1%
Cardiac disorders
Atrial fibrillation@ | 13 (4) | 4 (1)
Tachycardia | 6 (2) | < 1%
Cardiac failure congestive@ | 5 (1) | < 1%
Nervous system disorders
Syncope | 10 (3) | < 1%
Dizziness | 7 (2) | < 1%
Eye disorders
Cataract | 6 (2) | < 1%
Cataract unilateral | 5 (1) | 0 (0)
Psychiatric disorder
Depression | 10 (3) | 6 (2)

Table 8: Serious Adverse Reactions Reported in ≥1% Patients and with a ≥1% Difference in Proportion of Patients with MM between the REVLIMID/dexamethasone and Placebo/dexamethasone Groups
Body System Adverse Reaction | REVLIMID/Dex (N=353) n (%) | Placebo/Dex (N=350) n (%)
Blood and lymphatic system disorders
Febrile neutropenia% | 6 (2) | 0 (0)
Vascular disorders
Deep vein thrombosis% | 26 (7) | 11 (3)
Infections and infestations
Pneumonia@ | 33 (9) | 21 (6)
Respiratory, thoracic, and mediastinal disorders
Pulmonary embolism@ | 13 (4) | < 1%
Cardiac disorders
Atrial fibrillation@ | 11 (3) | < 1%
Cardiac failure congestive@ | 5 (1) | 0 (0)
Nervous system disorders
Cerebrovascular accident@ | 7 (2) | < 1%
Gastrointestinal disorders
Diarrhea @ | 6 (2) | < 1%
Musculoskeletal and connective tissue disorders
Bone pain | 4 (1) | 0 (0)
For Tables 6, 7 and 8 above:
@ - adverse reactions in which at least one resulted in a fatal outcome.
% - adverse reactions in which at least one was considered to be life threatening (if the outcome of the reaction was death, it is included with death cases).

Median duration of exposure among patients treated with REVLIMID/dexamethasone was 44 weeks while median duration of exposure among patients treated with placebo/dexamethasone was 23 weeks. This should be taken into consideration when comparing frequency of adverse reactions between two treatment groups REVLIMID/dexamethasone vs. placebo/dexamethasone.

Venous and Arterial Thromboembolism [see Boxed Warning, Warnings and Precautions (5.4)]

VTE and ATE are increased in patients treated with REVLIMID.

Deep vein thrombosis (DVT) was reported as a serious (7.4%) or severe (8.2%) adverse drug reaction at a higher rate in the REVLIMID/dexamethasone group compared to 3.1 % and 3.4% in the placebo/dexamethasone group, respectively in the 2 studies in patients with at least 1 prior therapy with discontinuations due to DVT adverse reactions reported at comparable rates between groups. In the NDMM study, DVT was reported as an adverse reaction (all grades: 10.3%, 7.2%, 4.1%), as a serious adverse reaction (3.6%, 2.0%, 1.7%), and as a Grade 3/4 adverse reaction (5.6%, 3.7%, 2.8%) in the Rd Continuous, Rd18, and MPT Arms, respectively. Discontinuations and dose reductions due to DVT adverse reactions were reported at comparable rates between the Rd Continuous and Rd18 Arms (both <1%). Interruption of REVLIMID treatment due to DVT adverse reactions was reported at comparable rates between the Rd Continuous (2.3%) and Rd18 (1.5%) arms. Pulmonary embolism (PE) was reported as a serious adverse drug reaction (3.7%) or Grade 3/4 (4.0%) at a higher rate in the REVLIMID/dexamethasone group compared to 0.9% (serious or grade 3/4) in the placebo/dexamethasone group in the 2 studies in patients with, at least 1 prior therapy, with discontinuations due to PE adverse reactions reported at comparable rates between groups. In the NDMM study, the frequency of adverse reactions of PE was similar between the Rd Continuous, Rd18, and MPT Arms for adverse reactions (all grades: 3.9%, 3.3%, and 4.3%, respectively), serious adverse reactions (3.8%, 2.8%, and 3.7%, respectively), and grade 3/4 adverse reactions (3.8%, 3.0%, and 3.7%, respectively).

Myocardial infarction was reported as a serious (1.7%) or severe (1.7%) adverse drug reaction at a higher rate in the REVLIMID/dexamethasone group compared to 0.6 % and 0.6% respectively in the placebo/dexamethasone group. Discontinuation due to MI (including acute) adverse reactions was 0.8% in REVLIMID/dexamethasone group and none in the placebo/dexamethasone group. In the NDMM study, myocardial infarction (including acute) was reported as an adverse reaction (all grades: 2.4%, 0.6%, and 1.1%), as a serious adverse reaction, (2.3%, 0.6%, and 1.1%), or as a severe adverse reaction (1.9%, 0.6%, and 0.9%) in the Rd Continuous, Rd18, and MPT Arms, respectively.

Stroke (CVA) was reported as a serious (2.3%) or severe (2.0%) adverse drug reaction in the REVLIMID/dexamethasone group compared to 0.9% and 0.9% respectively in the placebo/dexamethasone group. Discontinuation due to stroke (CVA) was 1.4% in REVLIMID/ dexamethasone group and 0.3% in the placebo/dexamethasone group. In the NDMM study, CVA was reported as an adverse reaction (all grades: 0.8%, 0.6%, and 0.6%), as a serious adverse reaction (0.8%, 0.6 %, and 0.6%), or as a severe adverse reaction (0.6%, 0.6%, 0.2%) in the Rd Continuous, Rd18, and MPT arms respectively.

Other Adverse Reactions: After At Least One Prior Therapy for MM

In these 2 studies, the following adverse drug reactions (ADRs) not described above that occurred at ≥1% rate and of at least twice of the placebo percentage rate were reported:

Blood and lymphatic system disorders: pancytopenia, autoimmune hemolytic anemia

Cardiac disorders: bradycardia, myocardial infarction, angina pectoris

Endocrine disorders: hirsutism

Eye disorders: blindness, ocular hypertension

Gastrointestinal disorders: gastrointestinal hemorrhage, glossodynia

General disorders and administration site conditions: malaise

Investigations: liver function tests abnormal, alanine aminotransferase increased

Nervous system disorders: cerebral ischemia

Psychiatric disorders: mood swings, hallucination, loss of libido

Reproductive system and breast disorders: erectile dysfunction

Respiratory, thoracic and mediastinal disorders: cough, hoarseness

Skin and subcutaneous tissue disorders: exanthem, skin hyperpigmentation

Myelodysplastic Syndromes:

A total of 148 patients received at least 1 dose of 10 mg REVLIMID in the del 5q MDS clinical study. At least one adverse reaction was reported in all of the 148 patients who were treated with the 10 mg starting dose of REVLIMID. The most frequently reported adverse reactions were related to blood and lymphatic system disorders, skin and subcutaneous tissue disorders, gastrointestinal disorders, and general disorders and administrative site conditions.

Thrombocytopenia (61.5%; 91/148) and neutropenia (58.8%; 87/148) were the most frequently reported adverse reactions. The next most common adverse reactions observed were diarrhea (48.6%; 72/148), pruritus (41.9%; 62/148), rash (35.8%; 53/148) and fatigue (31.1%; 46/148). Table 9 summarizes the adverse reactions that were reported in ≥ 5% of the REVLIMID treated patients in the del 5q MDS clinical study. Table 10 summarizes the most frequently observed Grade 3 and Grade 4 adverse reactions regardless of relationship to treatment with REVLIMID. In the single-arm studies conducted, it is often not possible to distinguish adverse reactions that are drug-related and those that reflect the patient's underlying disease.

Table 9: Summary of Adverse Reactions Reported in ≥5% of the REVLIMID Treated Patients in del 5q MDS Clinical Study
Body System Adverse Reaction a | 10 mg Overall (N=148)
Patients with at least one adverse reaction | 148 (100)
Blood and Lymphatic System Disorders
Thrombocytopenia | 91 (61)
Neutropenia | 87 (59)
Anemia | 17 (11)
Leukopenia | 12 (8)
Febrile Neutropenia | 8 (5)
Skin and Subcutaneous Tissue Disorders
Pruritus | 62 (42)
Rash | 53 (36)
Dry Skin | 21 (14)
Contusion | 12 (8)
Night Sweats | 12 (8)
Sweating Increased | 10 (7)
Ecchymosis | 8 (5)
Erythema | 8 (5)
Gastrointestinal Disorders
Diarrhea | 72 (49)
Constipation | 35 (24)
Nausea | 35 (24)
Abdominal Pain | 18 (12)
Vomiting | 15 (10)
Abdominal Pain Upper | 12 (8)
Dry Mouth | 10 (7)
Loose Stools | 9 (6)
Respiratory, Thoracic and Mediastinal Disorders
Nasopharyngitis | 34 (23)
Cough | 29 (20)
Dyspnea | 25 (17)
Pharyngitis | 23 (16)
Epistaxis | 22 (15)
Dyspnea Exertional | 10 (7)
Rhinitis | 10 (7)
Bronchitis | 9 (6)
General Disorders and Administration Site Conditions
Fatigue | 46 (31)
Pyrexia | 31 (21)
Edema Peripheral | 30 (20)
Asthenia | 22 (15)
Edema | 15 (10)
Pain | 10 (7)
Rigors | 9 (6)
Chest Pain | 8 (5)
Musculoskeletal and Connective Tissue Disorders
Arthralgia | 32 (22)
Back Pain | 31 (21)
Muscle Cramp | 27 (18)
Pain in Limb | 16 (11)
Myalgia | 13 (9)
Peripheral Swelling | 12 (8)
Nervous System Disorders
Dizziness | 29 (20)
Headache | 29 (20)
Hypoesthesia | 10 (7)
Dysgeusia | 9 (6)
Peripheral Neuropathy | 8 (5)
Infections and Infestations
Upper Respiratory Tract Infection | 22 (15)
Pneumonia | 17 (11)
Urinary Tract Infection | 16 (11)
Sinusitis | 12 (8)
Cellulitis | 8 (5)
Metabolism and Nutrition Disorders
Hypokalemia | 16 (11)
Anorexia | 15 (10)
Hypomagnesemia | 9 (6)
Investigations
Alanine Aminotransferase Increased | 12 (8)
Psychiatric Disorders
Insomnia | 15 (10)
Depression | 8 (5)
Renal and Urinary Disorders
Dysuria | 10 (7)
Vascular Disorders
Hypertension | 9 (6)
Endocrine Disorders
Acquired Hypothyroidism | 10 (7)
Cardiac Disorders
Palpitations | 8 (5)
a Body System and adverse reactions are coded using the MedDRA dictionary. Body System and adverse reactions are listed in descending order of frequency for the Overall column. A patient with multiple occurrences of an adverse reaction is counted only once under the applicable Body System/Adverse Reaction.

Table 10: Most Frequently Observed Grade 3 and 4 Adverse Reactions ^1 Regardless of Relationship to Study Drug Treatment in the del 5q MDS Clinical Study
Adverse Reactions ^2 | 10 mg (N=148)
Patients with at least one Grade 3/4 AE | 131 (89)
Neutropenia | 79 (53)
Thrombocytopenia | 74 (50)
Pneumonia | 11 (7)
Rash | 10 (7)
Anemia | 9 (6)
Leukopenia | 8 (5)
Fatigue | 7 (5)
Dyspnea | 7 (5)
Back Pain | 7 (5)
Febrile Neutropenia | 6 (4)
Nausea | 6 (4)
Diarrhea | 5 (3)
Pyrexia | 5 (3)
Sepsis | 4 (3)
Dizziness | 4 (3)
Granulocytopenia | 3 (2)
Chest Pain | 3 (2)
Pulmonary Embolism | 3 (2)
Respiratory Distress | 3 (2)
Pruritus | 3 (2)
Pancytopenia | 3 (2)
Muscle Cramp | 3 (2)
Respiratory Tract Infection | 2 (1)
Upper Respiratory Tract Infection | 2 (1)
Asthenia | 2 (1)
Multi-organ Failure | 2 (1)
Epistaxis | 2 (1)
Hypoxia | 2 (1)
Pleural Effusion | 2 (1)
Pneumonitis | 2 (1)
Pulmonary Hypertension | 2 (1)
Vomiting | 2 (1)
Sweating Increased | 2 (1)
Arthralgia | 2 (1)
Pain in Limb | 2 (1)
Headache | 2 (1)
Syncope | 2 (1)
^1 Adverse reactions with frequency ≥1% in the 10 mg Overall group. Grade 3 and 4 are based on National Cancer Institute Common Toxicity Criteria version 2.
^2 Adverse reactions are coded using the MedDRA dictionary. A patient with multiple occurrences of an adverse reaction is counted only once in the adverse reaction category.

In other clinical studies of REVLIMID in MDS patients, the following serious adverse reactions (regardless of relationship to study drug treatment) not described in Table 9 or 10 were reported:

Blood and lymphatic system disorders: warm type hemolytic anemia, splenic infarction, bone marrow depression, coagulopathy, hemolysis, hemolytic anemia, refractory anemia

Cardiac disorders: cardiac failure congestive, atrial fibrillation, angina pectoris, cardiac arrest, cardiac failure, cardio-respiratory arrest, cardiomyopathy, myocardial infarction, myocardial ischemia, atrial fibrillation aggravated, bradycardia, cardiogenic shock, pulmonary edema, supraventricular arrhythmia, tachyarrhythmia, ventricular dysfunction

Ear and labyrinth disorders: vertigo

Endocrine disorders: Basedow's disease

Gastrointestinal disorders: gastrointestinal hemorrhage, colitis ischemic, intestinal perforation, rectal hemorrhage, colonic polyp, diverticulitis, dysphagia, gastritis, gastroenteritis, gastroesophageal reflux disease, obstructive inguinal hernia, irritable bowel syndrome, melena, pancreatitis due to biliary obstruction, pancreatitis, perirectal abscess, small intestinal obstruction, upper gastrointestinal hemorrhage

General disorders and administration site conditions: disease progression, fall, gait abnormal, intermittent pyrexia, nodule, rigors, sudden death

Hepatobiliary disorders: hyperbilirubinemia, cholecystitis, acute cholecystitis, hepatic failure

Immune system disorders: hypersensitivity

Infections and infestations: infection bacteremia, central line infection, clostridial infection, ear infection, Enterobacter sepsis, fungal infection, herpes viral infection NOS, influenza, kidney infection, Klebsiella sepsis, lobar pneumonia, localized infection, oral infection, Pseudomonas infection, septic shock, sinusitis acute, sinusitis, Staphylococcal infection, urosepsis

Injury, poisoning and procedural complications: femur fracture, transfusion reaction, cervical vertebral fracture, femoral neck fracture, fractured pelvis, hip fracture, overdose, post procedural hemorrhage, rib fracture, road traffic accident, spinal compression fracture

Investigations: blood creatinine increased, hemoglobin decreased, liver function tests abnormal, troponin I increased

Metabolism and nutrition disorders: dehydration, gout, hypernatremia, hypoglycemia

Musculoskeletal and connective tissue disorders: arthritis, arthritis aggravated, gouty arthritis, neck pain, chondrocalcinosis pyrophosphate

Neoplasms benign, malignant and unspecified: acute leukemia, acute myeloid leukemia, bronchoalveolar carcinoma, lung cancer metastatic, lymphoma, prostate cancer metastatic

Nervous system disorders: cerebrovascular accident, aphasia, cerebellar infarction, cerebral infarction, depressed level of consciousness, dysarthria, migraine, spinal cord compression, subarachnoid hemorrhage, transient ischemic attack

Psychiatric disorders: confusional state

Renal and urinary disorders: renal failure, hematuria, renal failure acute, azotemia, calculus ureteric, renal mass

Reproductive system and breast disorders: pelvic pain

Respiratory, thoracic and mediastinal disorders: bronchitis, chronic obstructive airways disease exacerbated, respiratory failure, dyspnea exacerbated, interstitial lung disease, lung infiltration, wheezing

Skin and subcutaneous tissue disorders: acute febrile neutrophilic dermatosis

Vascular system disorders: deep vein thrombosis, hypotension, aortic disorder, ischemia, thrombophlebitis superficial, thrombosis

Mantle Cell Lymphoma:

In the MCL trial, a total of 134 patients received at least 1 dose of REVLIMID. Their median age was 67 (range 43-83) years, 128/134 (96%) were Caucasian, 108/134 (81%) were males and 82/134 (61%) had duration of MCL for at least 3 years.

Table 11 summarizes the most frequently observed adverse reactions regardless of relationship to treatment with REVLIMID. Across the 134 patients treated in this study, median duration of treatment was 95 days (1-1002 days). Seventy-eight patients (58%) received 3 or more cycles of therapy, 53 patients (40%) received 6 or more cycles, and 26 patients (19%) received 12 or more cycles. Seventy-six patients (57%) underwent at least one dose interruption due to adverse reactions, and 51 patients (38%) underwent at least one dose reduction due to adverse reactions. Twenty-six patients (19%) discontinued treatment due to adverse reactions.

Table 11: Incidence of Adverse Reactions (≥10%) or Grade 3 / 4 AE (in at least 2 patients) in Mantle Cell Lymphoma
Body System Adverse Reaction | All Adverse Reactions^1 (N=134) n (%) | Grade 3/4 Adverse Reactions^2 (N=134) n (%)
General disorders and administration site conditions
Fatigue | 45 (34) | 9 (7)
Pyrexia$ | 31 (23) | 3 (2)
Edema peripheral | 21 (16) | 0
Asthenia$ | 19 (14) | 4 (3)
General physical health deterioration | 3 (2) | 2 (1)
Gastrointestinal disorders
Diarrhea$ | 42 (31) | 8 (6)
Nausea$ | 40 (30) | 1 (<1)
Constipation | 21 (16) | 1 (<1)
Vomiting$ | 16 (12) | 1 (<1)
Abdominal pain$ | 13 (10) | 5 (4)
Musculoskeletal and connective tissue disorders
Back pain | 18 (13) | 2 (1)
Muscle spasms | 17 (13) | 1 (<1)
Arthralgia | 11 (8) | 2 (1)
Muscular weakness$ | 8 (6) | 2 (1)
Respiratory, thoracic and mediastinal disorders
Cough | 38 (28) | 1 (<1)
Dyspnea$ | 24 (18) | 8 (6)
Pleural Effusion | 10 (7) | 2 (1)
Hypoxia | 3 (2) | 2 (1)
Pulmonary embolism | 3 (2) | 2 (1)
Respiratory distress$ | 2 (1) | 2 (1)
Oropharyngeal pain | 13 (10) | 0
Infections and infestations
Pneumonia@ $ | 19 (14) | 12 (9)
Upper respiratory tract infection | 17 (13) | 0
Cellulitis$ | 3 (2) | 2 (1)
Bacteremia$ | 2 (1) | 2 (1)
Staphylococcal sepsis$ | 2 (1) | 2 (1)
Urinary tract infection$ | 5 (4) | 2 (1)
Skin and subcutaneous tissue disorders
Rash ^+ | 30 (22) | 2 (1)
Pruritus | 23 (17) | 1 (<1)
Blood and lymphatic system disorders
Neutropenia | 65 (49) | 58 (43)
Thrombocytopenia% $ | 48 (36) | 37 (28)
Anemia$ | 41 (31) | 15 (11)
Leukopenia$ | 20 (15) | 9 (7)
Lymphopenia | 10 (7) | 5 (4)
Febrile neutropenia$ | 8 (6) | 8 (6)
Metabolism and nutrition disorders
Decreased appetite | 19 (14) | 1 (<1)
Hypokalemia | 17 (13) | 3 (2)
Dehydration$ | 10 (7) | 4 (3)
Hypocalcemia | 4 (3) | 2 (1)
Hyponatremia | 3 (2) | 3 (2)
Renal and urinary disorders
Renal failure$ | 5 (4) | 2 (1)
Vascular disorders
Hypotension@ $ | 9 (7) | 4 (3)
Deep vein thrombosis$ | 5 (4) | 5 (4)
Neoplasms benign, malignant and unspecified (including cysts and polyps)
Tumor flare | 13 (10) | 0
Squamous cell carcinoma of skin$ | 4 (3) | 4 (3)
Investigations
Weight decreased | 17 (13) | 0
^1-MCL trial AEs – All treatment emergent AEs with ≥10% of subjects.
^2-MCL trial Grade 3/4 AEs – All treatment-emergent Grade 3/4 AEs in 2 or more subjects.
$-MCL trial Serious AEs – All treatment-emergent SAEs in 2 or more subjects.
@ - Adverse reactions where at least one resulted in a fatal outcome.
% - Adverse reactions where at least one was considered to be Life Threatening (if the outcome of the event was death, it is included with death cases).
# - All adverse reactions under Body System of Infections except for rare infections of Public Health interest will be considered listed.
^+ - All adverse reactions under HLT of Rash will be considered listed.

The following adverse reactions which have occurred in other indications including another MCL study and not described above have been reported (1%-10%) in patients treated with REVLIMID monotherapy for mantle cell lymphoma.

Cardiac disorder: Cardiac failure

Ear and labyrinth disorders: Vertigo

General disorders and administration site conditions: Chills

Infections and infestations: Respiratory tract infection, sinusitis, nasopharyngitis, oral herpes

Musculoskeletal and connective tissue disorders: Pain in extremity

Nervous system disorders: Dysgeusia, headache, neuropathy peripheral, lethargy

Psychiatric disorders: Insomnia

Skin and subcutaneous tissue disorders: Dry skin, night sweats

The following serious adverse reactions not described above and reported in 2 or more patients treated with REVLIMID monotherapy for mantle cell lymphoma.

Blood and lymphatic system disorders: Neutropenia

Cardiac disorder: Myocardial infarction (including acute MI), supraventricular tachycardia

Infections and infestations: Clostridium difficile colitis, sepsis

Neoplasms benign, malignant and unspecified (including cysts and polyps): Basal cell carcinoma

Respiratory, thoracic, and mediastinal disorders: Chronic obstructive pulmonary disease, pulmonary embolism

Follicular Lymphoma or Marginal Zone Lymphoma

The safety of REVLIMID/ rituximab was evaluated in 398 patients with either previously treated follicular lymphoma or marginal zone lymphoma in two clinical trials; AUGMENT (N=176) and MAGNIFY (N=222) [see Clinical Studies (14.4)]. Subjects were 18 years or older in age, had an ECOG PS ≤2, ANC ≥1,000 cells/mm^3 and platelets≥ 75,000/mm^3 (unless secondary to bone marrow involvement by lymphoma), hemoglobin ≥8g/dL, AST and ALT ≤ 3 x ULN (unless documented liver involvement with lymphoma, and creatinine clearance of ≥ 30mL/min. Subjects with active HIV, hepatitis B or C were not eligible.

In the AUGMENT trial, patients received REVLIMID 20 mg daily by mouth on days 1 – 21 of each 28 day cycle with rituximab 375 mg/m^2 weekly (days 1, 8, 15 and 22 in cycle 1) then on day 1 of cycles 2-5 (n=176) or placebo with rituximab 375 mg/m^2 weekly (days 1, 8, 15 and 22 in cycle 1) then on day 1 of cycles 2-5 (n=180) for up to 12 cycles. In the MAGNIFY trial, patients received REVLIMID 20 mg by mouth daily, days 1-21 of each 28 day cycle with rituximab 375 mg/m^2 weekly (days 1, 8, 15 and 22 in cycle 1) then on day 1 of cycles 3, 5, 7, 9 and 11 in the induction phase of the trial (n=222). In the AUGMENT trial, 88.1% of patients completed at least 6 cycles of REVLIMID/rituximab, and 71% of patients completed 12 cycles. In the ongoing MAGNIFY trial as of May 1, 2017, 62.2% of patients completed at least 6 cycles of REVLIMID/rituximab, and 30.6% of patients completed 12 cycles.

Across both clinical trials (AUGMENT and MAGNIFY), patients had a median age of 64.5 years (26 to 91); 49% were male; and 81% were White.

Fatal adverse reactions occurred in 6 patients (1.5%) receiving REVLIMID/rituximab. Fatal adverse reactions (1 each) included cardio-respiratory arrest, arrhythmia, cardiopulmonary failure, multiple organ dysfunction syndrome, sepsis, and acute kidney injury. Serious adverse reactions occurred in 26% of patients receiving REVLIMID/rituximab in AUGMENT and 29% in MAGNIFY. The most frequent serious adverse reaction that occurred in ≥ 2.5% of patients in the REVLIMID/rituximab arm was febrile neutropenia (3%). Permanent discontinuation of REVLIMID or rituximab due to an adverse reaction occurred in 14.6% of patients in the REVLIMID/rituximab arm. The most common adverse reaction (in at least 1%) requiring permanent discontinuation of REVLIMID or rituximab was neutropenia (4.8%).

The most common adverse reactions occurring in at least 20% of subjects were; neutropenia (48%), fatigue (37%), diarrhea (32%), constipation (27%), nausea (21%), and cough (20%).

Table 12: All Grade Adverse Reactions (≥5%) or Grade 3/4 Adverse Reactions (≥1%) in Patients with FL and MZL with a Difference Between Arms of >1% When Compared to Control Arm in AUGMENT Trial
 | All Adverse Reactions ^1 |  | Grade 3 / 4 Adverse Reactions ^2
Body System Adverse Reaction* | REVLIMID + Rituximab Arm (N=176) n (%) | Rituximab + Placebo (Control Arm) (N=180) n (%) | REVLIMID + Rituximab Arm (N=176) n (%) | Rituximab + Placebo (Control Arm) (N=180) n (%)
Infections and infestations
Upper respiratory tract infection | 32 (18) | 23 (13) | 2 (1.1) | 4 (2.2)
Influenza % | 17 (10) | 8 (4.4) | 1 (< 1) | 0 (0)
Pneumonia 3,$,% | 13 (7) | 6 (3.3) | 6 (3.4) | 4 (2.2)
Sinusitis | 13 (7) | 5 (2.8) | 0 (0) | 0 (0)
Urinary tract infection$ | 13 (7) | 7 (3.9) | 1 (< 1) | 1 (< 1)
Bronchitis | 8 (4.5) | 6 (3.3) | 2 (1.1) | 0 (0)
Gastroenteritis $ | 6 (3.4) | 4 (2.2) | 2 (1.1) | 0 (0)
Neoplasms benign, malignant and unspecified (including cysts and polyps)
Tumor flare $ | 19 (11) | 1 (< 1) | 1 (< 1) | 0 (0)
Blood and lymphatic disorders
Neutropenia 3,$, % | 102 (58) | 40 (22) | 88 (50) | 23 (13)
Leukopenia $,% | 36 (20) | 17 (9) | 12 (7) | 3 (1.7)
Anemia 3,$ | 28 (16) | 8 (4.4) | 8 (4.5) | 1 (< 1)
Thrombocytopenia 3,$,% | 26 (15) | 8 (4.4) | 4 (2.3) | 2 (1.1)
Lymphopenia | 8 (4.5) | 14 (8) | 5 (2.8) | 2 (1.1)
Febrile Neutropenia 3,$,% | 5 (2.8) | 1 (< 1) | 5 (2.8) | 1 (< 1)
Metabolism and nutrition disorders
Decreased Appetite | 23 (13) | 11 (6) | 2 (1.1) | 0 (0)
Hypokalemia % | 14 (8) | 5 (2.8) | 4 (2.3) | 0 (0)
Hyperuricemia | 10 (6) | 8 (4.4) | 1 (< 1) | 1 (< 1)
Nervous system disorders
Headache | 26 (15) | 17 (9) | 1 (< 1) | 0 (0)
Dizziness | 15 (9) | 9 (5) | 0 (0) | 0 (0)
Vascular disorders
Hypotension % | 9 (5) | 1 (< 1) | 1 (< 1) | 0 (0)
Thromboembolic events a,$ | 8 (4.5) | 2 (1.1) | 4 (2.3) | 2 (1.1)
Respiratory, thoracic and mediastinal disorders
Cough b | 43 (24) | 35 (19) | 1 (< 1) | 0 (0)
Dyspnea $ | 19 (11) | 8 (4.4) | 2 (1.1) | 1 (< 1)
Oropharyngeal pain | 10 (6) | 8 (4.4) | 0 (0) | 0 (0)
Pulmonary Embolism 3,$ | 4 (2.3) | 1 (< 1) | 4 (2.3) | 1 (< 1)
Chronic obstructive pulmonary disease $ | 3 (1.7) | 0 (0) | 2 (1.1) | 0 (0)
Respiratory failure 3,$ | 2 (1.1) | 1 (< 1) | 2 (1.1) | 0 (0)
Gastrointestinal disorders
Diarrhea $,% | 55 (31) | 41 (23) | 5 (2.8) | 0 (0)
Constipation | 46 (26) | 25 (14) | 0 (0) | 0 (0)
Abdominal pain c ,$ | 32 (18) | 20 (11) | 2 (1.1) | 0 (0)
Vomiting $ | 17 (10) | 13 (7) | 0 (0) | 0 (0)
Dyspepsia | 16 (9) | 5 (2.8) | 0 (0) | 0 (0)
Stomatitis | 9 (5) | 7 (3.9) | 0 (0) | 0 (0)
Skin and subcutaneous tissue disorders
Rash $,d | 39 (22) | 14 (8) | 5 (2.8) | 2 (1.1)
Pruritus $,e | 36 (20) | 9 (5) | 2 (1.1) | 0 (0)
Dry skin | 9 (5) | 6 (3.3) | 0 (0) | 0 (0)
Dermatitis acneiform | 8 (4.5) | 0 (0) | 2 (1.1) | 0 (0)
Musculoskeletal and connective tissue disorders
Muscle Spasms | 23 (13) | 9 (5) | 1 (< 1) | 1 (< 1)
Pain in Extremity $ | 8 (4.5) | 9 (5) | 2 (1) | 0 (0)
Renal disorders
Acute Kidney Injury 3,$,@,% | 3 (1.7) | 0 (0) | 2 (1.1) | 0 (0)
Cardiac disorders
Supraventricular tachycardia 3,$ | 2 (1.1) | 0 (0) | 2 (1.1) | 0 (0)
General disorders and administration site conditions
Fatigue | 38 (22) | 33 (18) | 2 (1.1) | 1 (< 1)
Pyrexia 3,$ | 37 (21) | 27 (15) | 1 (< 1) | 3 (1.7)
Asthenia $,% | 24 (14) | 19 (11) | 2 (1.1) | 1 (< 1)
Edema Peripheral $ | 23 (13) | 16 (9) | 0 (0) | 0 (0)
Chills | 14 (8) | 8 (4.4) | 0 (0) | 0 (0)
Malaise | 13 (7) | 10 (6) | 0 (0) | 0 (0)
Influenza like illness | 9 (5) | 7 (3.9) | 0 (0) | 0 (0)
Psychiatric disorders
Insomnia | 14 (8) | 11 (6) | 0 (0) | 0 (0)
Investigations
Alanine Aminotransferase Increased | 18 (10) | 15 (8) | 3 (1.7) | 1 (< 1)
WBC count decreased | 16 (9) | 13 (7) | 5 (2.8) | 2 (1.1)
Lymphocyte count decreased | 12 (7) | 12 (7) | 6 (3.4) | 2 (1.1)
Blood bilirubin increased | 10 (6) | 0 (0) | 0 (0) | 0 (0)
Weight Decreased | 12 (7) | 2 (1.1) | 0 (0) | 0 (0)
Note: Adverse reactions are coded to body system/adverse reaction using MedDRA 21. A patient with multiple occurrences of an adverse reaction is counted only once under the applicable Body System/Adverse reaction.
^1 All treatment-emergent AEs in at least 5% of patients in the REVLIMID + rituximab group and at least 1% higher frequency (%) than the rituximab + placebo group (control arm).
^2 All grade 3 or 4 treatment-emergent AEs in at least 1% of patients in the REVLIMID + rituximab group and at least 1% higher frequency (%) than the rituximab + placebo group (control arm).
^3 All serious treatment-emergent AEs in at least 1% of patients in the REVLIMID + rituximab group and at least 1% higher frequency (%) than the rituximab + placebo group (control arm).
$ Serious ADR reported.
@ - adverse reactions in which at least one resulted in a fatal outcome.
% - adverse reactions in which at least one was considered to be life threatening (if the outcome of the reaction was death, it is included with death cases).
*Adverse Reactions for combined ADR terms (based on relevant TEAE PTs [per MedDRA version 21.0]):
a "Thromboembolic events" combined term includes the following PTs: pulmonary embolism, deep vein thrombosis, cerebrovascular accident, embolism, and thrombosis.
b "Cough" combined AE term includes the following PTs: cough and productive cough.
c “Abdominal pain” combined AE term includes the following PTs: abdominal pain and abdominal pain upper.
d "Rash" combined AE term includes the following PTs: rash maculo-papular, rash erythematous, rash macular, rash papular, rash pruritic, and rash generalized.
e "Pruritus" combined AE term includes the following PTs: pruritus, pruritus generalized, rash pruritic, and pruritus allergic.

6.2 Postmarketing Experience

The following adverse drug reactions have been identified from the worldwide post-marketing experience with REVLIMID. Because these reactions are reported voluntarily from a population of uncertain size, it is not always possible to reliably estimate their frequency or establish a causal relationship to drug exposure [see Warnings and Precautions Section (5.8 to 5.11, and 5.13)]

Endocrine disorders: Hypothyroidism, hyperthyroidism

Hepatobiliary disorders: Hepatic failure (including fatality), toxic hepatitis, cytolytic hepatitis, cholestatic hepatitis, mixed cytolytic/cholestatic hepatitis, transient abnormal liver laboratory tests

Immune system disorders: Angioedema, anaphylaxis, acute graft-versus-host disease (following allogeneic hematopoietic transplant), solid organ transplant rejection

Infections and infestations: Viral reactivation (such as hepatitis B virus and herpes zoster), progressive multifocal leukoencephalopathy (PML)

Neoplasms benign, malignant and unspecified (including cysts and polyps): Tumor lysis syndrome, tumor flare reaction

Respiratory, thoracic and mediastinal disorders: Pneumonitis

Skin and subcutaneous tissue disorders: Stevens-Johnson Syndrome, toxic epidermal necrolysis, drug reaction with eosinophilia and systemic symptoms (DRESS)

7 DRUG INTERACTIONS

7.1 Digoxin

When digoxin was co-administered with multiple doses of REVLIMID (10 mg/day) the digoxin Cmax and AUCinf were increased by 14%. Periodically monitor digoxin plasma levels, in accordance with clinical judgment and based on standard clinical practice in patients receiving this medication, during administration of REVLIMID.

7.2 Concomitant Therapies That May Increase the Risk of Thrombosis

Erythropoietic agents, or other agents that may increase the risk of thrombosis, such as estrogen containing therapies, should be used with caution after making a benefit-risk assessment in patients receiving REVLIMID [see Warnings and Precautions (5.4)].

7.3 Warfarin

Co-administration of multiple doses of REVLIMID (10 mg/day) with a single dose of warfarin (25 mg) had no effect on the pharmacokinetics of lenalidomide or R- and S-warfarin. Expected changes in laboratory assessments of PT and INR were observed after warfarin administration, but these changes were not affected by concomitant REVLIMID administration. It is not known whether there is an interaction between dexamethasone and warfarin. Close monitoring of PT and INR is recommended in patients with MM taking concomitant warfarin.

8 USE IN SPECIFIC POPULATIONS

8.1 Pregnancy

Pregnancy Exposure Registry

There is a pregnancy exposure registry that monitors pregnancy outcomes in females exposed to REVLIMID during pregnancy as well as female partners of male patients who are exposed to REVLIMID. This registry is also used to understand the root cause for the pregnancy. Report any suspected fetal exposure to REVLIMID to the FDA via the MedWatch program at 1-800-FDA-1088 and also to the REMS Call Center at 1-888-423-5436.

Risk Summary

Based on the mechanism of action [see Clinical Pharmacology (12.1)] and findings from animal studies [see Data], REVLIMID can cause embryo-fetal harm when administered to a pregnant female and is contraindicated during pregnancy [see Boxed Warning, Contraindications (4.1), and Use in Specific Populations (5.1)].

REVLIMID is a thalidomide analogue. Thalidomide is a human teratogen, inducing a high frequency of severe and life-threatening birth defects such as amelia (absence of limbs), phocomelia (short limbs), hypoplasticity of the bones, absence of bones, external ear abnormalities (including anotia, micropinna, small or absent external auditory canals), facial palsy, eye abnormalities (anophthalmos, microphthalmos), and congenital heart defects. Alimentary tract, urinary tract, and genital malformations have also been documented and mortality at or shortly after birth has been reported in about 40% of infants.

Lenalidomide caused thalidomide-type limb defects in monkey offspring. Lenalidomide crossed the placenta after administration to pregnant rabbits and pregnant rats [see Data]. If this drug is used during pregnancy, or if the patient becomes pregnant while taking this drug, the patient should be apprised of the potential risk to a fetus.

If pregnancy does occur during treatment, immediately discontinue the drug. Under these conditions, refer patient to an obstetrician/gynecologist experienced in reproductive toxicity for further evaluation and counseling. Report any suspected fetal exposure to REVLIMID to the FDA via the MedWatch program at 1-800-FDA-1088 and also to the REMS Call Center at 1-888-423-5436.

The estimated background risk of major birth defects and miscarriage for the indicated population is unknown. All pregnancies have a background risk of birth defect, loss, or other adverse outcomes. The estimated background risk in the U.S. general population of major birth defects is 2%-4% and of miscarriage is 15%-20% of clinically recognized pregnancies.

Data

Animal data

In an embryo-fetal developmental toxicity study in monkeys, teratogenicity, including thalidomide-like limb defects, occurred in offspring when pregnant monkeys received oral lenalidomide during organogenesis. Exposure (AUC) in monkeys at the lowest dose was 0.17 times the human exposure at the maximum recommended human dose (MRHD) of 25 mg. Similar studies in pregnant rabbits and rats at 20 times and 200 times the MRHD respectively, produced embryo lethality in rabbits and no adverse reproductive effects in rats.

In a pre- and post-natal development study in rats, animals received lenalidomide from organogenesis through lactation. The study revealed a few adverse effects on the offspring of female rats treated with lenalidomide at doses up to 500 mg/kg (approximately 200 times the human dose of 25 mg based on body surface area). The male offspring exhibited slightly delayed sexual maturation and the female offspring had slightly lower body weight gains during gestation when bred to male offspring. As with thalidomide, the rat model may not adequately address the full spectrum of potential human embryo-fetal developmental effects for lenalidomide.

Following daily oral administration of lenalidomide from Gestation Day 7 through Gestation Day 20 in pregnant rabbits, fetal plasma lenalidomide concentrations were approximately 20-40% of the maternal Cmax. Following a single oral dose to pregnant rats, lenalidomide was detected in fetal plasma and tissues; concentrations of radioactivity in fetal tissues were generally lower than those in maternal tissues. These data indicated that lenalidomide crossed the placenta.

8.2 Lactation

Risk Summary

There is no information regarding the presence of lenalidomide in human milk, the effects of REVLIMID on the breastfed child, or the effects of REVLIMID on milk production. Because many drugs are excreted in human milk and because of the potential for adverse reactions in breastfed children from REVLIMID, advise women not to breastfeed during treatment with REVLIMID.

8.3 Females and Males of Reproductive Potential

Pregnancy Testing

REVLIMID can cause fetal harm when administered during pregnancy [see Use in Specific Populations (8.1)]. Verify the pregnancy status of females of reproductive potential prior to initiating REVLIMID therapy and during therapy. Advise females of reproductive potential that they must avoid pregnancy 4 weeks before therapy, while taking REVLIMID, during dose interruptions and for at least 4 weeks after completing therapy.

Females of reproductive potential must have 2 negative pregnancy tests before initiating REVLIMID. The first test should be performed within 10-14 days, and the second test within 24 hours prior to prescribing REVLIMID. Once treatment has started and during dose interruptions, pregnancy testing for females of reproductive potential should occur weekly during the first 4 weeks of use, then pregnancy testing should be repeated every 4 weeks in females with regular menstrual cycles. If menstrual cycles are irregular, the pregnancy testing should occur every 2 weeks. Pregnancy testing and counseling should be performed if a patient misses her period or if there is any abnormality in her menstrual bleeding. REVLIMID treatment must be discontinued during this evaluation.

Contraception

Females

Females of reproductive potential must commit either to abstain continuously from heterosexual sexual intercourse or to use 2 methods of reliable birth control simultaneously: one highly effective form of contraception – tubal ligation, IUD, hormonal (birth control pills, injections, hormonal patches, vaginal rings, or implants), or partner's vasectomy, and 1 additional effective contraceptive method – male latex or synthetic condom, diaphragm, or cervical cap. Contraception must begin 4 weeks prior to initiating treatment with REVLIMID, during therapy, during dose interruptions, and continuing for 4 weeks following discontinuation of REVLIMID therapy. Reliable contraception is indicated even where there has been a history of infertility, unless due to hysterectomy. Females of reproductive potential should be referred to a qualified provider of contraceptive methods, if needed.

Males

Lenalidomide is present in the semen of males who take REVLIMID. Therefore, males must always use a latex or synthetic condom during any sexual contact with females of reproductive potential while taking REVLIMID and for up to 4 weeks after discontinuing REVLIMID, even if they have undergone a successful vasectomy. Male patients taking REVLIMID must not donate sperm and for up to 4 weeks after discontinuing REVLIMID.

8.4 Pediatric Use

Safety and effectiveness have not been established in pediatric patients.

8.5 Geriatric Use

MM In Combination: Overall, of the 1613 patients in the NDMM study who received study treatment, 94% (1521 /1613) were 65 years of age or older, while 35% (561/1613) were over 75 years of age. The percentage of patients over age 75 was similar between study arms (Rd Continuous: 33%; Rd18: 34%; MPT: 33%). Overall, across all treatment arms, the frequency in most of the adverse reaction categories (eg, all adverse reactions, grade 3/4 adverse reactions, serious adverse reactions) was higher in older (> 75 years of age) than in younger (≤ 75 years of age) subjects. Grade 3 or 4 adverse reactions in the General Disorders and Administration Site Conditions body system were consistently reported at a higher frequency (with a difference of at least 5%) in older subjects than in younger subjects across all treatment arms. Grade 3 or 4 adverse reactions in the Infections and Infestations, Cardiac Disorders (including cardiac failure and congestive cardiac failure), Skin and Subcutaneous Tissue Disorders, and Renal and Urinary Disorders (including renal failure) body systems were also reported slightly, but consistently, more frequently (<5% difference), in older subjects than in younger subjects across all treatment arms. For other body systems (e.g., Blood and Lymphatic System Disorders, Infections and Infestations, Cardiac Disorders, Vascular Disorders), there was a less consistent trend for increased frequency of grade 3/4 adverse reactions in older vs younger subjects across all treatment arms Serious adverse reactions were generally reported at a higher frequency in the older subjects than in the younger subjects across all treatment arms.

MM Maintenance Therapy: Overall, 10% (106/1018) of patients were 65 years of age or older, while no patients were over 75 years of age. Grade 3 or 4 adverse reactions were higher in the REVLIMID arm (more than 5% higher) in the patients 65 years of age or older versus younger patients. The frequency of Grade 3 or 4 adverse reactions in the Blood and Lymphatic System Disorders were higher in the REVLIMID arm (more than 5% higher) in the patients 65 years of age or older versus younger patients. There were not a sufficient number of patients 65 years of age or older in REVLIMID maintenance studies who experienced either a serious adverse reaction, or discontinued therapy due to an adverse reaction to determine whether elderly patients respond relative to safety differently from younger patients.

MM After At Least One Prior Therapy: Of the 703 MM patients who received study treatment in Studies 1 and 2, 45% were age 65 or over while 12% of patients were age 75 and over. The percentage of patients age 65 or over was not significantly different between the REVLIMID/dexamethasone and placebo/dexamethasone groups. Of the 353 patients who received REVLIMID/dexamethasone, 46% were age 65 and over. In both studies, patients > 65 years of age were more likely than patients ≤ 65 years of age to experience DVT, pulmonary embolism, atrial fibrillation, and renal failure following use of REVLIMID. No differences in efficacy were observed between patients over 65 years of age and younger patients.

Of the 148 patients with del 5q MDS enrolled in the major study, 38% were age 65 and over, while 33% were age 75 and over. Although the overall frequency of adverse reactions (100%) was the same in patients over 65 years of age as in younger patients, the frequency of serious adverse reactions was higher in patients over 65 years of age than in younger patients (54% vs. 33%). A greater proportion of patients over 65 years of age discontinued from the clinical studies because of adverse reactions than the proportion of younger patients (27% vs. 16%). No differences in efficacy were observed between patients over 65 years of age and younger patients.

Of the 134 patients with MCL enrolled in the MCL trial, 63% were age 65 and over, while 22% of patients were age 75 and over. The overall frequency of adverse reactions was similar in patients over 65 years of age and in younger patients (98% vs. 100%). The overall incidence of grade 3 and 4 adverse reactions was also similar in these 2 patient groups (79% vs. 78%, respectively). The frequency of serious adverse reactions was higher in patients over 65 years of age than in younger patients (55% vs. 41%). No differences in efficacy were observed between patients over 65 years of age and younger patients.

FL or MZL in Combination: Overall, 48% (282/590) of patients were 65 years of age or older, while 14% (82/590) of patients were over 75 years of age. The overall frequency of adverse reactions was similar in patients 65 years of age or older and younger patients for both studies pooled (98%). Grade 3 or 4 adverse reactions were higher in the REVLIMID arm (more than 5% higher) in the patients 65 years of age or older versus younger patients (71% versus 59%). The frequency of Grade 3 or 4 adverse reactions were higher in the REVLIMID arm (more than 5% higher) in the patients 65 years of age or older versus younger patients in the Blood and Lymphatic System Disorders (47% versus 40%) and Infections and Infestations (16% versus 11%). Serious adverse reactions were higher in the REVLIMID arm (more than 5% higher) in the patients 65 years of age or older versus younger patients (37% versus 18%). The frequency of serious adverse reactions were higher in the REVLIMID arm (more than 5% higher) in the patients 65 years of age or older versus younger patients in Infections and Infestations (15% versus 6%).

Since elderly patients are more likely to have decreased renal function, care should be taken in dose selection. Monitor renal function.

8.6 Renal Impairment

Adjust the starting dose of REVLIMID based on the creatinine clearance value and for patients on dialysis [see Dosage and Administration (2.6)].

10 OVERDOSAGE

There is no specific experience in the management of REVLIMID overdose in patients with MM, MDS, MCL, FL, or MZL. In dose-ranging studies in healthy subjects, some were exposed to up to 200 mg (administered 100 mg BID) and in single-dose studies, some subjects were exposed to up to 400 mg. Pruritus, urticaria, rash, and elevated liver transaminases were the primary reported AEs. In clinical trials, the dose-limiting toxicity was neutropenia and thrombocytopenia.

11 DESCRIPTION

REVLIMID, a thalidomide analogue, is an immunomodulatory agent with antiangiogenic and antineoplastic properties. The chemical name is 3-(4-amino-1-oxo 1,3-dihydro-2H-isoindol-2-yl) piperidine-2,6-dione and it has the following chemical structure:

3-(4-amino-1-oxo 1,3-dihydro-2H-isoindol-2-yl) piperidine-2,6-dione

The empirical formula for lenalidomide is C13H13N3O3, and the gram molecular weight is 259.3.

Lenalidomide is an off-white to pale-yellow solid powder. It is soluble in organic solvent/water mixtures, and buffered aqueous solvents. Lenalidomide is more soluble in organic solvents and low pH solutions. Solubility was significantly lower in less acidic buffers, ranging from about 0.4 to 0.5 mg/ml. Lenalidomide has an asymmetric carbon atom and can exist as the optically active forms S(-) and R(+), and is produced as a racemic mixture with a net optical rotation of zero.

REVLIMID is available in 2.5 mg, 5 mg, 10 mg, 15 mg, 20 mg and 25 mg capsules for oral administration. Each capsule contains lenalidomide as the active ingredient and the following inactive ingredients: lactose anhydrous, microcrystalline cellulose, croscarmellose sodium, and magnesium stearate. The 5 mg and 25 mg capsule shell contains gelatin, titanium dioxide and black ink. The 2.5 mg and 10 mg capsule shell contains gelatin, FD&C blue #2, yellow iron oxide, titanium dioxide and black ink. The 15 mg capsule shell contains gelatin, FD&C blue #2, titanium dioxide and black ink. The 20 mg capsule shell contains gelatin, FD&C blue #2, yellow iron oxide, titanium dioxide and black ink.

12 CLINICAL PHARMACOLOGY

12.1 Mechanism of Action

Lenalidomide is an analogue of thalidomide with immunomodulatory, antiangiogenic, and antineoplastic properties. Cellular activities of lenalidomide are mediated through its target cereblon, a component of a cullin ring E3 ubiquitin ligase enzyme complex. In vitro, in the presence of drug, substrate proteins (including Aiolos, Ikaros, and CK1α) are targeted for ubiquitination and subsequent degradation leading to direct cytotoxic and immunomodulatory effects. Lenalidomide inhibits proliferation and induces apoptosis of certain hematopoietic tumor cells including MM, mantle cell lymphoma, and del (5q) myelodysplastic syndromes, follicular lymphoma and marginal zone lymphoma in vitro. Lenalidomide causes a delay in tumor growth in some in vivo nonclinical hematopoietic tumor models including MM. Immunomodulatory properties of lenalidomide include increased number and activation of T cells and natural killer (NK) cells leading to direct and enhanced antibody-dependent cell-mediated cytotoxicity (ADCC) via increased secretion of interleukin-2 and interferon-gamma, increased numbers of NKT cells, and inhibition of pro-inflammatory cytokines (e.g., TNF-α and IL-6) by monocytes. In MM cells, the combination of lenalidomide and dexamethasone synergizes the inhibition of cell proliferation and the induction of apoptosis. The combination of lenalidomide and rituximab increases ADCC and direct tumor apoptosis in follicular lymphoma cells and increases ADCC in marginal zone lymphoma cells compared to rituximab alone in vitro.

12.2 Pharmacodynamics

Cardiac Electrophysiology

The effect of lenalidomide on the QTc interval was evaluated in 60 healthy male subjects in a thorough QT study. At a dose two times the maximum recommended dose, lenalidomide did not prolong the QTc interval. The largest upper bound of the two-sided 90% CI for the mean differences between lenalidomide and placebo was below 10 ms.

12.3 Pharmacokinetics

Absorption

Following single and multiple doses of REVLIMID in patients with MM or MDS, the maximum plasma concentrations occurred between 0.5 and 6 hours post-dose. The single and multiple dose pharmacokinetic disposition of lenalidomide is linear with AUC and Cmax values increasing proportionally with dose. Multiple doses of REVLIMID at the recommended dosage does not result in drug accumulation.

Administration of a single 25 mg dose of REVLIMID with a high-fat meal in healthy subjects reduces the extent of absorption, with an approximate 20% decrease in AUC and 50% decrease in Cmax. In the trials where the efficacy and safety were established for REVLIMID, the drug was administered without regard to food intake. REVLIMID can be administered with or without food.

The oral absorption rate of lenalidomide in patients with MCL is similar to that observed in patients with MM or MDS.

Distribution

In vitro [^14C]-lenalidomide binding to plasma proteins is approximately 30%.

Lenalidomide is present in semen at 2 hours (1379 ng/ejaculate) and 24 hours (35 ng/ejaculate) after the administration of REVLIMID 25 mg daily.

Elimination

The mean half-life of lenalidomide is 3 hours in healthy subjects and 3 to 5 hours in patients with MM, MDS or MCL.

Metabolism

Lenalidomide undergoes limited metabolism. Unchanged lenalidomide is the predominant circulating component in humans. Two identified metabolites are 5-hydroxy-lenalidomide and N-acetyl-lenalidomide; each constitutes less than 5% of parent levels in circulation.

Excretion

Elimination is primarily renal. Following a single oral administration of [^14C]-lenalidomide 25 mg to healthy subjects, approximately 90% and 4% of the radioactive dose was eliminated within ten days in urine and feces, respectively. Approximately 82% of the radioactive dose was excreted as lenalidomide in the urine within 24 hours. Hydroxy-lenalidomide and N-acetyl-lenalidomide represented 4.6% and 1.8% of the excreted dose, respectively. The renal clearance of lenalidomide exceeds the glomerular filtration rate.

Specific Populations

Renal Impairment: Eight subjects with mild renal impairment (creatinine clearance (CLcr) 50 to 79 mL/min calculated using Cockcroft-Gault), 9 subjects with moderate renal impairment (CLcr 30 to 49 mL/min), 4 subjects with severe renal impairment (CLcr < 30 mL/min), and 6 patients with end stage renal disease (ESRD) requiring dialysis were administered a single 25 mg dose of REVLIMID. Three healthy subjects of similar age with normal renal function (CLcr > 80 mL/min) were also administered a single 25 mg dose of REVLIMID. As CLcr decreased, half-life increased and drug clearance decreased linearly. Patients with moderate and severe impairment had a 3-fold increase in half-life and a 66% to 75% decrease in drug clearance compared to healthy subjects. Patients on hemodialysis (n=6) had an approximate 4.5-fold increase in half-life and an 80% decrease in drug clearance compared to healthy subjects. Approximately 30% of the drug in body was removed during a 4-hour hemodialysis session.

Adjust the starting dose of REVLIMID in patients with renal impairment based on the CLcr value [see Dosage and Administration (2.6)].

Hepatic Impairment: Mild hepatic impairment (defined as total bilirubin > 1 to 1.5 times upper limit normal (ULN) or any aspartate transaminase greater than ULN) did not influence the disposition of lenalidomide. No pharmacokinetic data is available for patients with moderate to severe hepatic impairment.

Other Intrinsic Factors: Age (39 to 85 years), body weight (33 to 135 kg), sex, race, and type of hematological malignancies (MM, MDS or MCL) did not have a clinically relevant effect on lenalidomide clearance in adult patients.

Drug Interactions

Co-administration of a single dose or multiple doses of dexamethasone (40 mg) had no clinically relevant effect on the multiple dose pharmacokinetics of REVLIMID (25 mg).

Co-administration of REVLIMID (25 mg) after multiple doses of a P-gp inhibitor such as quinidine (600 mg twice daily) did not significantly increase the Cmax or AUC of lenalidomide.

Co-administration of the P-gp inhibitor and substrate temsirolimus (25 mg),with REVLIMID (25 mg) did not significantly alter the pharmacokinetics of lenalidomide, temsirolimus, or sirolimus (metabolite of temsirolimus).

In vitro studies demonstrated that REVLIMID is a substrate of P-glycoprotein (P-gp). REVLIMID is not a substrate of human breast cancer resistance protein (BCRP), multidrug resistance protein (MRP) transporters MRP1, MRP2, or MRP3, organic anion transporters (OAT) OAT1 and OAT3, organic anion transporting polypeptide 1B1 (OATP1B1), organic cation transporters (OCT) OCT1 and OCT2, multidrug and toxin extrusion protein (MATE) MATE1, and organic cation transporters novel (OCTN) OCTN1 and OCTN2. Lenalidomide is not an inhibitor of P-gp, bile salt export pump (BSEP), BCRP, MRP2, OAT1, OAT3, OATP1B1, OATP1B3, or OCT2. Lenalidomide does not inhibit or induce CYP450 isoenzymes. Also, lenalidomide does not inhibit bilirubin glucuronidation formation in human liver microsomes with UGT1A1 genotyped as UGT1A1*1/*1, UGT1A1*1/*28, and UGT1A1*28/*28.

13 NONCLINICAL TOXICOLOGY

13.1 Carcinogenesis, Mutagenesis, Impairment of Fertility

Carcinogenicity studies with lenalidomide have not been conducted.

Lenalidomide was not mutagenic in the bacterial reverse mutation assay (Ames test) and did not induce chromosome aberrations in cultured human peripheral blood lymphocytes, or mutations at the thymidine kinase (tk) locus of mouse lymphoma L5178Y cells. Lenalidomide did not increase morphological transformation in Syrian Hamster Embryo assay or induce micronuclei in the polychromatic erythrocytes of the bone marrow of male rats.

A fertility and early embryonic development study in rats, with administration of lenalidomide up to 500 mg/kg (approximately 200 times the human dose of 25 mg, based on body surface area) produced no parental toxicity and no adverse effects on fertility.

14 CLINICAL STUDIES

14.1 Multiple Myeloma

Randomized, Open-Label Clinical Trial in Patients with Newly Diagnosed MM:

A randomized multicenter, open-label, 3-arm trial of 1,623 patients, was conducted to compare the efficacy and safety of REVLIMID and low-dose dexamethasone (Rd) given for 2 different durations of time to that of melphalan, prednisone and thalidomide (MPT) in newly diagnosed MM patients who were not a candidate for stem cell transplant. In the first arm of the study, Rd was given continuously until progressive disease [Arm Rd Continuous]. In the second arm, Rd was given for up to eighteen 28-day cycles [72 weeks, Arm Rd18]). In the third arm, melphalan, prednisone and thalidomide (MPT) was given for a maximum of twelve 42-day cycles (72 weeks). For the purposes of this study, a patient who was < 65 years of age was not a candidate for SCT if the patient refused to undergo SCT therapy or the patient did not have access to SCT due to cost or other reasons. Patients were stratified at randomization by age (≤75 versus >75 years), stage (ISS Stages I and II versus Stage III), and country.

Patients in the Rd Continuous and Rd18 arms received REVLIMID 25 mg once daily on Days 1 to 21 of 28-day cycles. Dexamethasone was dosed 40 mg once daily on Days 1, 8, 15, and 22 of each 28-day cycle. For patients over > 75 years old, the starting dose of dexamethasone was 20 mg orally once daily on days 1,8,15, and 22 of repeated 28-day cycles. Initial dose and regimens for Rd Continuous and Rd18 were adjusted according to age and renal function. All patients received prophylactic anticoagulation with the most commonly used being aspirin.

The demographics and disease-related baseline characteristics of the patients were balanced among the 3 arms. In general, study subjects had advanced-stage disease. Of the total study population, the median age was 73 in the 3 arms with 35% of total patients > 75 years of age; 59% had ISS Stage I/II; 41% had ISS stage III; 9% had severe renal impairment (creatinine clearance [CLcr] < 30 mL/min); 23% had moderate renal impairment (CLcr > 30 to 50 mL/min; 44% had mild renal impairment (CLcr > 50 to 80 mL/min). For ECOG Performance Status, 29% were Grade 0, 49% Grade 1, 21% Grade 2, 0.4% ≥ Grade 3.

The primary efficacy endpoint, progression-free survival (PFS), was defined as the time from randomization to the first documentation of disease progression as determined by Independent Response Adjudication Committee (IRAC), based on International Myeloma Working Group [IMWG] criteria or death due to any cause, whichever occurred first during the study until the end of the PFS follow-up phase. For the efficacy analysis of all endpoints, the primary comparison was between Rd Continuous and MPT arms. The efficacy results are summarized in the table below. PFS was significantly longer with Rd Continuous than MPT: HR 0.72 (95% CI: 0.61-0.85 p <0.0001). A lower percentage of subjects in the Rd Continuous arm compared with the MPT arm had PFS events (52% versus 61%, respectively). The improvement in median PFS time in the Rd Continuous arm compared with the MPT arm was 4.3 months. The myeloma response rate was higher with Rd Continuous compared with MPT (75.1% versus 62.3%); with a complete response in 15.1% of Rd Continuous arm patients versus 9.3% in the MPT arm. The median time to first response was 1.8 months in the Rd Continuous arm versus 2.8 months in the MPT arm.

For the interim OS analysis with 03 March 2014 data cutoff, the median follow-up time for all surviving patients is 45.5 months, with 697 death events, representing 78% of prespecified events required for the planned final OS analysis (697/896 of the final OS events). The observed OS HR was 0.75 for Rd Continuous versus MPT (95% CI = 0.62, 0.90).

Table 13: Overview of Efficacy Results – Study MM-020 (Intent-to-treat Population)
 | Rd Continuous (N = 535) | Rd18 (N = 541) | MPT (N = 547)
PFS – IRAC (months)g
Number of PFS events | 278 (52) | 348 (64.3) | 334 (61.1)
Mediana PFS time, months (95% CI)b | 25.5 (20.7, 29.4) | 20.7 (19.4, 22) | 21.2 (19.3, 23.2)
HR [95% CI]c; p-valued
Rd Continuous vs MPT | 0.72 (0.61, 0.85); <0.0001
Rd Continuous vs Rd18 | 0.70 (0.60, 0.82)
Rd18 vs MPT | 1.03 (0.89, 1.20)
Overall Survival (months)h
Number of Death events | 208 (38.9) | 228 (42.1) | 261 (47.7)
Mediana OS time, months (95% CI)b | 58.9 (56, NE)f | 56.7 (50.1, NE) | 48.5 (44.2, 52)
HR [95% CI]c
Rd Continuous vs MPT | 0.75 (0.62, 0.90)
Rd Continuous vs Rd18 | 0.91 (0.75, 1.09)
Rd18 vs MPT | 0.83 (0.69, 0.99)
Response Ratee – IRAC, n (%)g
CR | 81 (15.1) | 77 (14.2) | 51 (9.3)
VGPR | 152 (28.4) | 154 (28.5) | 103 (18.8)
PR | 169 (31.6) | 166 (30.7) | 187 (34.2)
Overall response: CR, VGPR, or PR | 402 (75.1) | 397 (73.4) | 341 (62.3)
CR = complete response; d = low-dose dexamethasone; HR = hazard ratio; IRAC = Independent Response Adjudication Committee; M = melphalan; NE = not estimable; OS = overall survival; P = prednisone; PFS = progression-free survival; PR = partial response; R = REVLIMID; Rd Continuous = Rd given until documentation of progressive disease; Rd18 = Rd given for ≤ 18 cycles; T = thalidomide; VGPR = very good partial response; vs = versus.
a The median is based on the Kaplan-Meier estimate.
b The 95% Confidence Interval (CI) about the median.
c Based on Cox proportional hazards model comparing the hazard functions associated with the indicated treatment arms.
d The p-value is based on the unstratified log-rank test of Kaplan-Meier curve differences between the indicated treatment arms.
e Best assessment of response during the treatment phase of the study.
f Including patients with no response assessment data or whose only assessment was "response not evaluable."
g Data cutoff date = 24 May 2013.
h Data cutoff date = 3 March 2014.

Kaplan-Meier Curves of Progression-free Survival Based on IRAC Assessment (ITT MM Population) Between Arms Rd Continuous, Rd18 and MPT
Cutoff date: 24 May 2013

CI = confidence interval; d = low-dose dexamethasone; HR = hazard ratio; IRAC = Independent Response Adjudication Committee; M = melphalan; P = prednisone; R = REVLIMID; Rd Continuous = Rd given until documentation of progressive disease; Rd18 = Rd given for ≤ 18 cycles; T = thalidomide.

Kaplan-Meier Curves of Overall Survival (ITT MM Population) Between Arms Rd Continuous, Rd18 and MPT
Cutoff date: 03 Mar 2014

CI = confidence interval; d = low-dose dexamethasone; HR = hazard ratio; M = melphalan; P = prednisone; R = REVLIMID; Rd Continuous = Rd given until documentation of progressive disease; Rd18 = Rd given for ≤18 cycles; T = thalidomide.

Randomized, Placebo-Controlled Clinical Trials - Maintenance Following Auto-HSCT:

Two multicenter, randomized, double-blind, parallel group, placebo-controlled studies were conducted to evaluate the efficacy and safety of REVLIMID maintenance therapy in the treatment of MM patients after auto-HSCT. In Maintenance Study 1, patients between 18 and 70 years of age who had undergone induction therapy followed by auto-HSCT were eligible. Induction therapy must have occurred within 12 months. Within 90-100 days after auto-HSCT, patients with at least a stable disease response were randomized 1:1 to receive either REVLIMID or placebo maintenance. In Maintenance Study 2, patients aged < 65 years at diagnosis who had undergone induction therapy followed by auto-HSCT and had achieved at least a stable disease response at the time of hematologic recovery were eligible. Within 6 months after auto-HSCT, patients were randomized 1:1 to receive either REVLIMID or placebo maintenance. Patients eligible for both trials had to have CLcr ≥30 mL/minute.

In both studies, the REVLIMID maintenance dose was 10 mg once daily on days 1-28 of repeated 28-day cycles, could be increased to 15 mg once daily after 3 months in the absence of dose-limiting toxicity, and treatment was to be continued until disease progression or patient withdrawal for another reason. The dose was reduced, or treatment was temporarily interrupted or stopped, as needed to manage toxicity. A dose increase to 15 mg once daily occurred in 135 patients (58%) in Maintenance Study 1, and in 185 patients (60%) in Maintenance Study 2.

The demographics and disease-related baseline characteristics of the patients were similar across the two studies and reflected a typical MM population after auto-HSCT (see Table 14).

Table 14: Baseline Demographic and Disease-Related Characteristics – MM Maintenance Studies 1 and 2
 | Maintenance Study 1 |  | Maintenance Study 2
 | REVLIMID N = 231 | Placebo N = 229 | REVLIMID N = 307 | Placebo N = 307
Age (years)
Median | 58 | 58 | 57.5 | 58.1
(Min, max) | (29, 71) | (39, 71) | (22.7, 68.3) | (32.3, 67)
Sex, n (%)
Male | 121 (52) | 129 (56) | 169 (55) | 181 (59)
Female | 110 (48) | 100 (44) | 138 (45) | 126 (41)
ISS Stage at Diagnosis, n (%)
Stage I or II | 120 (52) | 131 (57) | 232 (76) | 250 (81)
Stage I | 62 (27) | 85 (37) | 128 (42) | 143 (47)
Stage II | 58 (25) | 46 (20) | 104 (34) | 107 (35)
Stage III | 39 (17) | 35 (15) | 66 (21) | 46 (15)
Missing | 72 (31) | 63 (28) | 9 (3) | 11 (4)
CrCl at Post-auto-HSCT, n (%)
< 50 mL/min | 23 (10) | 16 (7) | 10 (3) | 9 (3)
≥ 50 mL/min | 201 (87) | 204 (89) | 178 (58) | 200 (65)
Missing | 7 (3) | 9 (4) | 119 (39) | 98 (32)
Data cutoff date = 1 March 2015.

The major efficacy endpoint of both studies was PFS defined from randomization to the date of progression or death, whichever occurred first; the individual studies were not powered for an overall survival endpoint. Both studies were unblinded upon the recommendations of their respective data monitoring committees and after surpassing the respective thresholds for preplanned interim analyses of PFS. After unblinding, patients continued to be followed as before. Patients in the placebo arm of Maintenance Study 1 were allowed to cross over to receive REVLIMID before disease progression (76 patients [33%] crossed over to REVLIMID); patients in Maintenance Study 2 were not recommended to cross over. The efficacy results are summarized in the following table. In both studies, the primary analysis of PFS at unblinding was significantly longer with REVLIMID compared to placebo: Maintenance Study 1 HR 0.38 (95% CI: 0.27-0.54 p <0.001) and Maintenance Study 2 HR 0.50 (95% CI: 0.39-0.64 p <0.001). For both studies, PFS was updated with a cutoff date of 1 March 2015 as shown in the table and the following Kaplan Meier graphs. With longer follow-up (median 72.4 and 86.0 months, respectively), the updated PFS analyses for both studies continue to show a PFS advantage for REVLIMID compared to placebo: Maintenance Study 1 HR 0.38 (95% CI: 0.28-0.50) with median PFS of 68.6 months and Maintenance Study 2 HR 0.53 (95% CI: 0.44-0.64) with median PFS of 46.3 months.

Descriptive analysis of OS data with a cutoff date of 1 February 2016 are provided in Table 15. Median follow-up time was 81.6 and 96.7 months for Maintenance Study 1 and Maintenance Study 2, respectively. Median OS was 111.0 and 84.2 months for REVLIMID and placebo, respectively, for Maintenance Study 1, and 105.9 and 88.1 months, for REVLIMID and placebo, respectively, for Maintenance Study 2.

Table 15: Progression-free Survival and Overall Survival from Randomization in MM Maintenance Studies 1 and 2 (ITT Post-Auto-HSCT Population)
 | Maintenance Study 1 |  | Maintenance Study 2
 | REVLIMID N = 231 | Placebo N = 229 | REVLIMID N = 307 | Placebo N = 307
PFS at Unblinding
PFS Events n (%) | 46 (20) | 98 (43) | 103 (34) | 160 (52)
Median in months [95% CI] | 33.9 [NE, NE] | 19 [16.2, 25.6] | 41.2 [38.3, NE] | 23.0 [21.2, 28.0]
Hazard Ratio [95% CI] | 0.38 [0.27, 0.54] |  | 0.50 [0.39, 0.64]
Log-rank Test p-value | <0.001 |  | <0.001
PFS at Updated Analysis 1 March 2015 (Studies 1 and 2)
PFS Events n (%) | 97 (42) | 116 (51) | 191 (62) | 248 (81)
Median in months [95% CI] | 68.6 [52.8, NE] | 22.5 [18.8, 30.0] | 46.3 [40.1, 56.6] | 23.8 [21.0, 27.3]
Hazard Ratio [95% CI] | 0.38 [0.28, 0.50] |  | 0.53 [0.44, 0.64]
OS at Updated Analysis 1 Feb 2016 (Studies 1 and 2)
OS Events n (%) | 82 (35) | 114 (50) | 143 (47) | 160 (52)
Median in months [95% CI] | 111 [101.8, NE] | 84.2 [71.0, 102.7] | 105.9 [88.8, NE] | 88.1 [80.7, 108.4]
Hazard Ratio [95% CI] | 0.59 [0.44, 0.78] |  | 0.90 [0.72, 1.13]
Date of Unblinding in Maintenance Study 1 and 2 = 17 December 2009 and 7 July 2010, respectively.
Auto-HSCT = autologous hematopoietic stem cell transplantation; CI = confidence interval; ITT = intent to treat; NE = not estimable; PFS = progression-free survival.
PFS at time of unblinding for Maintenance Study 2 was based on assessment by an Independent Review Committee. All other PFS analyses were based on assessment by investigator.
Note: The median is based on Kaplan-Meier estimate, with 95% CIs about the median overall PFS time. Hazard ratio is based on a proportional hazards model stratified by stratification factors comparing the hazard functions associated with treatment arms (REVLIMID:placebo).

Kaplan-Meier Curves of Progression-free Survival from Randomization (ITT Post-Auto-HSCT Population) in MM Maintenance Study 1 between REVLIMID and Placebo Arms (Updated Cutoff Date 1 March 2015)

Auto-HSCT = autologous hematopoietic stem cell transplantation; CI = confidence interval; HR = hazard ratio; ITT = intent to treat; KM = Kaplan-Meier; PFS = progression-free survival; vs = versus.

Kaplan-Meier Curves of Progression-free Survival from Randomization (ITT Post-Auto-HSCT Population) in MM Maintenance Study 2 between REVLIMID and Placebo Arms (Updated Cutoff Date 1 March 2015)

Auto-HSCT = autologous hematopoietic stem cell transplantation; CI = confidence interval; HR = hazard ratio; ITT = intent to treat; KM = Kaplan-Meier; NE = not estimable; PFS = progression-free survival; vs = versus.

Randomized, Open-Label Clinical Studies in Patients with MM After At Least One Prior Therapy

Two randomized studies (Studies 1 and 2) were conducted to evaluate the efficacy and safety of REVLIMID. These multicenter, multinational, double-blind, placebo-controlled studies compared REVLIMID plus oral pulse high-dose dexamethasone therapy to dexamethasone therapy alone in patients with MM who had received at least one prior treatment. These studies enrolled patients with absolute neutrophil counts (ANC) ≥ 1000/mm^3, platelet counts ≥ 75,000/mm^3, serum creatinine ≤ 2.5 mg/dL, serum SGOT/AST or SGPT/ALT ≤ 3 x upper limit of normal (ULN), and serum direct bilirubin ≤ 2 mg/dL.

In both studies, patients in the REVLIMID/dexamethasone group took 25 mg of REVLIMID orally once daily on Days 1 to 21 and a matching placebo capsule once daily on Days 22 to 28 of each 28-day cycle. Patients in the placebo/dexamethasone group took 1 placebo capsule on Days 1 to 28 of each 28-day cycle. Patients in both treatment groups took 40 mg of dexamethasone orally once daily on Days 1 to 4, 9 to 12, and 17 to 20 of each 28-day cycle for the first 4 cycles of therapy.

The dose of dexamethasone was reduced to 40 mg orally once daily on Days 1 to 4 of each 28-day cycle after the first 4 cycles of therapy. In both studies, treatment was to continue until disease progression.

In both studies, dose adjustments were allowed based on clinical and laboratory findings. Sequential dose reductions to 15 mg daily, 10 mg daily and 5 mg daily were allowed for toxicity [see Dosage and Administration (2.1)].

Table 16 summarizes the baseline patient and disease characteristics in the two studies. In both studies, baseline demographic and disease-related characteristics were comparable between the REVLIMID/dexamethasone and placebo/dexamethasone groups.

Table 16: Baseline Demographic and Disease-Related Characteristics – MM Studies 1 and 2
 | Study 1 |  | Study 2
 | REVLIMID/Dex N=177 | Placebo/Dex N=176 | REVLIMID/Dex N=176 | Placebo/Dex N=175
Patient Characteristics
Age (years)
Median | 64 | 62 | 63 | 64
Min, Max | 36, 86 | 37, 85 | 33, 84 | 40, 82
Sex
Male | 106 (60%) | 104 (59%) | 104 (59%) | 103 (59%)
Female | 71 (40%) | 72 (41%) | 72 (41%) | 72 (41%)
Race/Ethnicity
White | 141(80%) | 148 (84%) | 172 (98%) | 175 (100%)
Other | 36 (20%) | 28 (16%) | 4 (2%) | 0 (0%)
ECOG Performance
Status 0-1 | 157 (89%) | 168 (95%) | 150 (85%) | 144 (82%)
Disease Characteristics
Multiple Myeloma Stage (Durie-Salmon)
I | 3% | 3% | 6% | 5%
II | 32% | 31% | 28% | 33%
III | 64% | 66% | 65% | 63%
β2-microglobulin (mg/L)
≤ 2.5 mg/L | 52 (29%) | 51 (29%) | 51 (29%) | 48 (27%)
> 2.5 mg/L | 125 (71%) | 125 (71%) | 125 (71%) | 127 (73%)
Number of Prior Therapies
1 | 38% | 38% | 32% | 33%
≥ 2 | 62% | 62% | 68% | 67%
Types of Prior Therapies
Stem Cell Transplantation | 62% | 61% | 55% | 54%
Thalidomide | 42% | 46% | 30% | 38%
Dexamethasone | 81% | 71% | 66% | 69%
Bortezomib | 11% | 11% | 5% | 4%
Melphalan | 33% | 31% | 56% | 52%
Doxorubicin | 55% | 51% | 56% | 57%

The primary efficacy endpoint in both studies was time to progression (TTP). TTP was defined as the time from randomization to the first occurrence of progressive disease.

Preplanned interim analyses of both studies showed that the combination of REVLIMID/dexamethasone was significantly superior to dexamethasone alone for TTP. The studies were unblinded to allow patients in the placebo/dexamethasone group to receive treatment with the REVLIMID/dexamethasone combination. For both studies, the extended follow-up survival data with crossovers were analyzed. In study 1, the median survival time was 39.4 months (95%CI: 32.9, 47.4) in REVLIMID/dexamethasone group and 31.6 months (95% CI: 24.1, 40.9) in placebo/dexamethasone group, with a hazard ratio of 0.79 (95% CI: 0.61-1.03). In study 2, the median survival time was 37.5 months (95%CI: 29.9, 46.6) in REVLIMID/dexamethasone group and 30.8 months (95%CI: 23.5, 40.3) in placebo/dexamethasone group, with a hazard ratio of 0.86 (95% CI: 0.65-1.14).

Table 17: TTP Results in MM Study 1 and Study 2
 | Study 1 |  | Study 2
 | REVLIMID/Dex N=177 | Placebo/Dex N=176 | REVLIMID/Dex N=176 | Placebo/Dex N=175
TTP
Events n (%) | 73 (41) | 120 (68) | 68 (39) | 130 (74)
Median TTP in months [95% CI] | 13.9 [9.5, 18.5] | 4.7 [3.7, 4.9] | 12.1 [9.5, NE] | 4.7 [3.8, 4.8]
Hazard Ratio [95% CI] | 0.285 [0.210, 0.386] |  | 0.324 [0.240, 0.438]
Log-rank Test p-value 3 | <0.001 |  | <0.001
Response
Complete Response (CR) n (%) | 23 (13) | 1 (1) | 27 (15) | 7 (4)
Partial Response (RR/PR) n (%) | 84 (48) | 33 (19) | 77 (44) | 34 (19)
Overall Response n (%) | 107 (61) | 34 (19) | 104 (59) | 41 (23)
p-value | <0.001 |  | <0.001
Odds Ratio [95% CI] | 6.38 [3.95, 10.32] |  | 4.72 [2.98, 7.49]

Kaplan-Meier Estimate of Time to Progression — MM Study 1

Kaplan-Meier Estimate of Time to Progression — MM Study 2

14.2 Myelodysplastic Syndromes (MDS) with a Deletion 5q Cytogenetic Abnormality

The efficacy and safety of REVLIMID were evaluated in patients with transfusion-dependent anemia in low- or intermediate-1- risk MDS with a 5q (q31-33) cytogenetic abnormality in isolation or with additional cytogenetic abnormalities, at a dose of 10 mg once daily or 10 mg once daily for 21 days every 28 days in an open-label, single-arm, multi-center study. The major study was not designed nor powered to prospectively compare the efficacy of the 2 dosing regimens. Sequential dose reductions to 5 mg daily and 5 mg every other day, as well as dose delays, were allowed for toxicity [Dosage and Administration (2.2)].

This major study enrolled 148 patients who had RBC transfusion dependent anemia. RBC transfusion dependence was defined as having received ≥ 2 units of RBCs within 8 weeks prior to study treatment. The study enrolled patients with absolute neutrophil counts (ANC) ≥ 500/mm^3, platelet counts ≥ 50,000/mm^3, serum creatinine ≤ 2.5 mg/dL, serum SGOT/AST or SGPT/ALT ≤ 3 x upper limit of normal (ULN), and serum direct bilirubin ≤ 2 mg/dL. Granulocyte colony-stimulating factor was permitted for patients who developed neutropenia or fever in association with neutropenia. Baseline patient and disease-related characteristics are summarized in Table 18.

Table 18: Baseline Demographic and Disease-Related Characteristics in the MDS Study
 |  | Overall (N=148)
Age (years)
Median |  | 71
Min, Max |  | 37, 95
Gender | n | (%)
Male | 51 | (34.5)
Female | 97 | (65.5)
Race | n | (%)
White | 143 | (96.6)
Other | 5 | (3.4)
Duration of MDS (years)
Median |  | 2.5
Min, Max |  | 0.1, 20.7
Del 5 (q31-33) Cytogenetic Abnormality | n | (%)
Yes | 148 | (100)
Other cytogenetic abnormalities | 37 | (25.2)
IPSS Score a | n | (%)
Low (0) | 55 | (37.2)
Intermediate-1 (0.5-1.0) | 65 | (43.9)
Intermediate-2 (1.5-2.0) | 6 | (4.1)
High (≥2.5) | 2 | (1.4)
Missing | 20 | (13.5)
FAB Classification b from central review | n | (%)
RA | 77 | (52)
RARS | 16 | (10.8)
RAEB | 30 | (20.3)
CMML | 3 | (2)
a IPSS Risk Category: Low (combined score = 0), Intermediate-1 (combined score = 0.5 to 1), Intermediate-2 (combined score = 1.5 to 2.0), High (combined score ≥ 2.5); Combined score = (Marrow blast score + Karyotype score + Cytopenia score).
b French-American-British (FAB) classification of MDS.

The frequency of RBC transfusion independence was assessed using criteria modified from the International Working Group (IWG) response criteria for MDS. RBC transfusion independence was defined as the absence of any RBC transfusion during any consecutive "rolling" 56 days (8 weeks) during the treatment period.

Transfusion independence was seen in 99/148 (67%) patients (95% CI [59, 74]). The median duration from the date when RBC transfusion independence was first declared (i.e., the last day of the 56-day RBC transfusion-free period) to the date when an additional transfusion was received after the 56-day transfusion-free period among the 99 responders was 44 weeks (range of 0 to >67 weeks). Ninety percent of patients who achieved a transfusion benefit did so by completion of three months in the study.

RBC transfusion independence rates were unaffected by age or gender.

The dose of REVLIMID was reduced or interrupted at least once due to an adverse event in 118 (79.7%) of the 148 patients; the median time to the first dose reduction or interruption was 21 days (mean, 35.1 days; range, 2-253 days), and the median duration of the first dose interruption was 22 days (mean, 28.5 days; range, 2-265 days). A second dose reduction or interruption due to adverse events was required in 50 (33.8%) of the 148 patients. The median interval between the first and second dose reduction or interruption was 51 days (mean, 59.7 days; range, 15-205 days) and the median duration of the second dose interruption was 21 days (mean, 26 days; range, 2-148 days).

14.3 Mantle Cell Lymphoma

A multicenter, single-arm, open-label trial of single-agent REVLIMID was conducted to evaluate the safety and efficacy of REVLIMID in patients with mantle cell lymphoma who have relapsed after or were refractory to bortezomib or a bortezomib-containing regimen. Patients with a creatinine clearance ≥60 mL/min were given REVLIMID at a dose of 25 mg once daily for 21 days every 28 days. Patients with a creatinine clearance ≥30 mL/min and <60 mL/min were given REVLIMID at a dose of 10 mg once daily for 21 days every 28 days. Treatment was continued until disease progression, unacceptable toxicity, or withdrawal of consent.

The trial included patients who were at least 18 years of age with biopsy-proven MCL with measurable disease by CT scan. Patients were required to have received prior treatment with an anthracycline or mitoxantrone, cyclophosphamide, rituximab, and bortezomib, alone or in combination. Patients were required to have documented refractory disease (defined as without any response of PR or better during treatment with bortezomib or a bortezomib-containing regimen), or relapsed disease (defined as progression within one year after treatment with bortezomib or a bortezomib-containing regimen). At enrollment patients were to have an absolute neutrophil counts (ANC) ≥1500/ mm^3, platelet counts ≥ 60,000/mm^3, serum SGOT/AST or SGPT/ALT ≤3 x upper limit of normal (ULN) unless there was documented evidence of liver involvement by lymphoma, serum total bilirubin ≤1.5 x ULN except in cases of Gilbert's syndrome or documented liver involvement by lymphoma, and calculated creatinine clearance (Cockcroft-Gault formula) ≥30 mL/min.

The median age was 67 years (43-83), 81% were male and 96% were Caucasian. The table below summarizes the baseline disease-related characteristics and prior anti-lymphoma therapy in the Mantle Cell Lymphoma trial.

Table 19: Baseline Disease-related Characteristics and Prior Anti –Lymphoma Therapy in Mantle Cell Lymphoma Trial
Baseline Disease Characteristics and Prior Anti -Lymphoma Treatment | Total Patients (N=134)
ECOG Performance Statusa n (%)
0 | 43 (32)
1 | 73 (54)
2 | 17 (13)
3 | 1 (<1)
Advanced MCL Stage, n (%)
III | 27 (20)
IV | 97 (72)
High or Intermediate MIPI Score b, n (%) | 90 (67)
High Tumor Burdenc, n (%) | 77 (57)
Bulky Diseased, n (%) | 44 (33)
Extranodal Disease, n (%) | 101 (75)
Number of Prior Systemic Anti-Lymphoma Therapies, n (%)
Median (range) | 4 (2, 10)
1 | 0 (0)
2 | 29 (22)
3 | 34 (25)
≥ 4 | 71 (53)
Number of Subjects Who Received Prior Regimen Containing, n (%):
Anthracycline/mitoxantrone | 133 (99)
Cyclophosphamide | 133 (99)
Rituximab | 134 (100)
Bortezomib | 134 (100)
Refractory to Prior Bortezomib, n (%) | 81 (60)
Refractory to Last Prior Therapy, n (%) | 74 (55)
Prior Autologous Bone Marrow or Stem Cell Transplant, n (%) | 39 (29)
a ECOG = Eastern Cooperative Oncology Group.
b MIPI = MCL International Prognostic Index.
c High tumor burden is defined as at least one lesion that is ≥5 cm in diameter or 3 lesions that are ≥3 cm in diameter.
d Bulky disease is defined as at least one lesion that is ≥7cm in the longest diameter.

The efficacy endpoints in the MCL trial were overall response rate (ORR) and duration of response (DOR). Response was determined based on review of radiographic scans by an independent review committee according to a modified version of the International Workshop Lymphoma Response Criteria (Cheson, 1999). The DOR is defined as the time from the initial response (at least PR) to documented disease progression. The efficacy results for the MCL population were based on all evaluable patients who received at least one dose of study drug and are presented in Table 20. The median time to response was 2.2 months (range 1.8 to 13 months).

Table 20: Response Outcomes in the Pivotal Mantle Cell Lymphoma Trial
Response Analyses (N = 133) |  | N (%) | 95% CI
Overall Response Rate (IWRC) (CR + CRu +PR) |  | 34 (26) | (18.4, 33.9)
Complete Response (CR + CRu) |  | 9 (7) | (3.1, 12.5)
CR |  | 1 (1)
CRu |  | 8 (6)
Partial Response (PR) |  | 25 (19)
Duration of Response (months) |  | Median | 95% CI
Duration of Overall Response (CR + CRu + PR) | (N = 34) | 16.6 | (7.7, 26.7)

14.4 Follicular and Marginal Zone Lymphoma

The efficacy of REVLIMID with rituximab in patients with relapsed or refractory follicular and marginal zone lymphoma was evaluated in the AUGMENT (NCT01938001) and MAGNIFY (NCT01996865) trials.

AUGMENT is a randomized, double-blind, multicenter trial (n=358) in which patients with relapsed or refractory follicular or marginal zone lymphoma were randomized 1:1 to receive REVLIMID and rituximab or rituximab and placebo. AUGMENT included patients diagnosed with Grade 1, 2, or 3a follicular lymphoma, who received at least 1 prior systemic therapy, were refractory or relapsed, not rituximab-refractory, had at least one measurable nodal or extranodal lesion by CT or MRI scan, and had adequate bone marrow, liver, and renal function. Randomization was stratified by follicular versus marginal zone lymphoma, previous rituximab therapy, and time since other anti-lymphoma therapy. In AUGMENT, REVLIMID was administered orally 20 mg once daily for Days 1 to 21 of repeating 28-day cycles for a maximum of 12 cycles or until unacceptable toxicity. The dose of rituximab was 375 mg/m^2 every week in Cycle 1 (Days 1, 8, 15, and 22) and on Day 1 of every 28-day cycle from Cycles 2 through 5. All dosage calculations for rituximab were based on the patient's body surface area (BSA), using actual patient weight. Dose adjustments for REVLIMID were allowed based on clinical and laboratory findings. A patient with moderate renal insufficiency (≥30 to <60 mL/minute) received a lower REVLIMID starting dose of 10 mg daily on the same schedule. After 2 cycles, the REVLIMID dose could be increased to 15 mg once daily on Days 1 to 21 of each 28-day cycle if the patient tolerated the medication.

MAGNIFY is an open-label, multicenter trial (n=232) in which patients with relapsed or refractory follicular, marginal zone, or mantle cell lymphoma received 12 induction cycles of REVLIMID and rituximab. MAGNIFY included patients diagnosed with Grade 1, 2,3a, 3b follicular (including transformed), marginal zone, or mantle cell lymphoma Stage I to IV who were previously treated for their lymphoma, had been refractory or had a relapse after their last treatment, had at least one measurable nodal or extranodal lesion by CT or MRI scan, and had adequate bone marrow, liver, and renal function. Patients refractory to rituximab were also included. The information from the subjects who received at least 1 dose of initial therapy in the first 12 induction cycles (n=222) in the MAGNIFY trial was included in the evaluation of the efficacy of REVLIMID/rituximab in patients with relapsed or refractory follicular and marginal zone lymphoma. In MAGNIFY, REVLIMID 20 mg was given on Days 1-21 of repeated 28-day cycles for up to 12 cycles or until unacceptable toxicity, progression, or withdrawal of consent. The dose of rituximab was 375 mg/m^2 every week in Cycle 1 (Days 1, 8, 15, and 22) and on Day 1 of every other 28-day cycle (Cycles 3,5,7,9, and 11) up to 12 cycles therapy. All dosage calculations for rituximab were based on the patient BSA and actual weight. Dose adjustments were allowed based on clinical and laboratory findings.

The demographic and disease-related baseline characteristics in the AUGMENT and MAGNIFY trials are shown in the following table.

Table 21: Baseline Demographics and Disease-Related Characteristics of Patients with FL and MZL in AUGMENT and MAGNIFY Trials
Parameter | AUGMENT Trial |  | MAGNIFY Trial
Parameter | REVLIMID + Rituximab (N=178) | Rituximab + Placebo (Control Arm) (N=180) | REVLIMID + Rituximab (N=222)
Age (years)
Median (Max, Min) | 64 (26, 86) | 62 (35, 88) | 65 (35, 91)
Age distribution, n (%)
<65 years | 96 (54) | 107 (59) | 103 (46)
≥65 years | 82 (46) | 73 (41) | 119 (54)
Sex, n (%)
Male | 75 (42) | 97 (54) | 122 (55)
Female | 103 (58) | 83 (46) | 100 (45)
Race
White | 118 (66) | 115 (64) | 206 (93)
Other races | 54 (30) | 64 (36) | 14 (6)
Not collected or reported | 6 (3) | 1 (0.6) | 2 (1)
Body Surface Area (BSA, m^2)
Median (Max, Min) | 1.8 (1.4, 3.1) | 1.8 (1.3, 2.7) | 2 (1.3, 2.6)
Disease Type FL or MZL
Follicular lymphoma | 147 (83) | 148 (82) | 177 (80)
Marginal zone lymphoma | 31 (17) | 32 (18) | 45 (20)
MZL subtype at diagnosis (investigator), n (%)
MALT | 14 (45) | 16 (50) | 10 (22)
Nodal | 8 (26) | 10 (31) | 25 (56)
Splenic | 9 (29) | 6 (19) | 10 (22)
FL stage at diagnosis (investigator), n (%)
FL Grade 1-2 | 125 (85) | 123 (83) | 149 (84)
FL Grade 3a | 22 (15) | 25 (17) | 28 (16)
FLIPI score at baseline (calculated), n (%) |  |  | Not Collected
Low risk (0,1) | 52 (29) | 67 (37) | Not Collected
Intermediate risk (2) | 55 (31) | 58 (32) | Not Collected
High risk (≥3) | 69 (39) | 54 (30) | Not Collected
Missing | 2 (1) | 1 (0.6) | Not Collected
ECOG score at baseline, n (%)
0 | 116 (65) | 128 (71) | 102 (46)
1 | 60 (34) | 50 (28) | 113 (51)
2 | 2 (1) | 2 (1) | 7 (3)
High tumor burdena at baseline, n (%)
Yes | 97 (54) | 86 (48) | 148 (67)
No | 81 (46) | 94 (52) | 74 (33)
Number of prior systemic antilymphoma therapies
1 | 102 (57) | 97 (54) | 94 (42)b
>1 | 76 (43) | 83 (46) | 128 (58)
Data Cutoff: 22 June 2018 (AUGMENT) and 1 May 2017 (MAGNIFY).
a Defined by GELF criteria.
b Patient had either 0 (n=2) or 1 prior systemic therapy.
ECOG = Eastern Cooperative Oncology Group; FLIPI = follicular lymphoma international prognostic index

In AUGMENT, efficacy was established in the intent-to-treat (ITT) population based on progression-free survival by Independent Review Committee using modified 2007 International Working Group response criteria. Efficacy results are summarized in Table 22.

Table 22: Efficacy Results for Patients in the AUGMENT Trial (ITT FL and MZL Population)
Parameter | REVLIMID + Rituximab (N=178) | Rituximab + Placebo (N=180)
PFS
Patients with event, n (%) | 68 (38.2) | 115 (63.9)
Death | 6 (8.8) | 2 (1.7)
Progression of disease | 62 (91.2) | 113 (98.3)
PFS, median a [95% CI] (months) | 39.4 [ 22.9, NE] | 14.1 [11.4, 16.7]
HR b [95% CI] | 0.46 [ 0.34, 0.62]
p-value c | <0.0001
Objective response (CR+PR) , n(%) [95% CI] d | 138 (77.5) [70.7, 83.4] | 96 (53.3) [45.8, 60.8]
a Median estimate is from Kaplan-Meier analysis.
b hazard ratio and its CI were estimated from Cox proportional hazard model adjusting for the stratification 3: previous rituximab treatment (yes, no), time since last antilymphoma therapy (≤ 2, > 2 years), and disease histology (FL, MZL).
c p-value from log-rank test stratified by 3 factors noted above: previous rituximab treatment (yes, no), time since last antilymphoma therapy (≤ 2, > 2 years), and disease histology (FL, MZL).
d Exact confidence interval for binomial distribution.

Kaplan-Meier Curves of Progression-free Survival by IRC Assessment Between Arms in AUGMENT Trial (ITT FL and MZL Population)

a = Stratification factors included: previous rituximab treatment (y/n), time since last anti-lymphoma therapy (≤2 years, >2years), and disease histology (FL or MZL). CI = confidence interval; HR = hazard ratio; KM = Kaplan-Meier; PFS = progression-free survival

Follicular Lymphoma

In AUGMENT, the objective response by IRC assessment for patients with follicular lymphoma was 80% (118/147) [95% CI: 73%, 86%]) in REVLIMID with rituximab arm compared to 55% (82/148) [95% CI: 47, 64] in control arm.

In MAGNIFY, the overall response by investigator assessment was 59% (104/177) [95% CI: 51, 66] for patients with follicular lymphoma. Median duration of response was not reached with a median follow-up time of 7.9 months [95% CI: 4.6, 9.2].

Marginal Zone Lymphoma

In AUGMENT, the objective response by IRC assessment for patients with marginal zone lymphoma was 65% (20/31) [95% CI: 45%, 81%] in REVLIMID with rituximab arm compared to 44% (14/32) [95% CI: 26%, 62%] in control arm.

In MAGNIFY, the overall response by investigator assessment was 51% (23/45) [95% CI: 36, 66] for patients with marginal zone lymphoma. Median duration of response was not reached with a median follow-up time of 11.5 months [95% CI: 8.0, 18.9].

15 REFERENCES

1. OSHA Hazardous Drugs. OSHA [Accessed on 29 January 2013, from http://www.osha.gov/SLTC/hazardousdrugs/index.html]

16 HOW SUPPLIED/STORAGE AND HANDLING

16.1 How Supplied

White and blue-green opaque hard capsules imprinted "REV" on one half and "2.5 mg" on the other half in black ink:

 | 2.5 mg bottles of 28 | (NDC 59572-402-28)
 | 2.5 mg bottles of 100 | (NDC 59572-402-00)

White opaque capsules imprinted "REV" on one half and "5 mg" on the other half in black ink:

 | 5 mg bottles of 28 | (NDC 59572-405-28)
 | 5 mg bottles of 100 | (NDC 59572-405-00)

Blue/green and pale yellow opaque capsules imprinted "REV" on one half and "10 mg" on the other half in black ink:

 | 10 mg bottles of 28 | (NDC 59572-410-28)
 | 10 mg bottles of 100 | (NDC 59572-410-00)

Powder blue and white opaque capsules imprinted "REV" on one half and "15 mg" on the other half in black ink:

 | 15 mg bottles of 21 | (NDC 59572-415-21)
 | 15 mg bottles of 100 | (NDC 59572-415-00)

Powder blue and blue-green opaque hard capsules imprinted "REV" on one half and "20 mg" on the other half in black ink.

 | 20 mg bottles of 21 | (NDC 59572-420-21)
 | 20 mg bottles of 100 | (NDC 59572-420-00)

White opaque capsules imprinted "REV" on one half and "25 mg" on the other half in black ink:

 | 25 mg bottles of 21 | (NDC 59572-425-21)
 | 25 mg bottles of 100 | (NDC 59572-425-00)

16.2 Storage

Store at 20°C - 25°C (68°F - 77°F); excursions permitted to 15°C - 30°C (59°F - 86°F) [See USP Controlled Room Temperature].

16.3 Handling and Disposal

Care should be exercised in the handling of REVLIMID. REVLIMID capsules should not be opened or broken. If powder from REVLIMID contacts the skin, wash the skin immediately and thoroughly with soap and water. If REVLIMID contacts the mucous membranes, flush thoroughly with water.

Procedures for the proper handling and disposal of anticancer drugs should be considered. Several guidelines on the subject have been published.^1

Dispense no more than a 28-day supply.

17 PATIENT COUNSELING INFORMATION

Advise the patient to read the FDA-approved Patient labeling (Medication Guide)

Embryo-Fetal Toxicity

Advise patients that REVLIMID is contraindicated in pregnancy [see Boxed Warning and Contraindications (4.1)]. REVLIMID is a thalidomide analogue and can cause serious birth defects or death to a developing baby [see Warnings and Precautions (5.1) and Use in Specific Populations (8.1)].

- Advise females of reproductive potential that they must avoid pregnancy while taking REVLIMID and for at least 4 weeks after completing therapy.
- Initiate REVLIMID treatment in females of reproductive potential only following a negative pregnancy test.
- Advise females of reproductive potential of the importance of monthly pregnancy tests and the need to use 2 different forms of contraception including at least 1 highly effective form, simultaneously during REVLIMID therapy, during dose interruption and for 4 weeks after she has completely finished taking REVLIMID. Highly effective forms of contraception other than tubal ligation include IUD and hormonal (birth control pills, injections, patch or implants) and a partner's vasectomy. Additional effective contraceptive methods include latex or synthetic condom, diaphragm and cervical cap.
- Instruct patient to immediately stop taking REVLIMID and contact her healthcare provider if she becomes pregnant while taking this drug, if she misses her menstrual period, or experiences unusual menstrual bleeding, if she stops taking birth control, or if she thinks FOR ANY REASON that she may be pregnant.
- Advise patient that if her healthcare provider is not available, she should call the REMS Call Center at 1-888-423-5436 [see Warnings and Precautions (5.1) and Use in Specific Populations (8.3)].
- Advise males to always use a latex or synthetic condom during any sexual contact with females of reproductive potential while taking REVLIMID and for up to 4 weeks after discontinuing REVLIMID, even if they have undergone a successful vasectomy.
- Advise male patients taking REVLIMID that they must not donate sperm and for up to 4 weeks after discontinuation of REVLIMID [see Warnings and Precautions (5.1) and Use in Specific Populations (8.3)].
- All patients must be instructed to not donate blood while taking REVLIMID, during dose interruptions and for 4 weeks following discontinuation of REVLIMID [see Warnings and Precautions (5.1)].

Lenalidomide REMS program

Because of the risk of embryo-fetal toxicity, REVLIMID is only available through a restricted program called the Lenalidomide REMS program [see Warnings and Precautions (5.2)].

- Patients must sign a Patient-Physician agreement form and comply with the requirements to receive REVLIMID. In particular, females of reproductive potential must comply with the pregnancy testing, contraception requirements and participate in monthly telephone surveys. Males must comply with the contraception requirements [see Use in Specific Populations (8.3)].
- REVLIMID is available only from pharmacies that are certified in the Lenalidomide REMS program. Provide patients with the telephone number and website for information on how to obtain the product.

Pregnancy Exposure Registry

Inform females there is a Pregnancy Exposure Registry that monitors pregnancy outcomes in females exposed to REVLIMID during pregnancy and that they can contact the Pregnancy Exposure Registry by calling 1-888-423-5436 [see Use in Specific Populations (8.1)].

Hematologic Toxicity

Inform patients that REVLIMID is associated with significant neutropenia and thrombocytopenia [see Boxed Warning and Warnings and Precautions (5.3)].

Venous and Arterial Thromboembolism

Inform patients of the risk of thrombosis including DVT, PE, MI, and stroke and to report immediately any signs and symptoms suggestive of these events for evaluation [see Boxed Warning and Warnings and Precautions (5.4)].

Increased Mortality in Patients with CLL

Inform patients that REVLIMID had increased mortality in patients with CLL and serious adverse cardiovascular reactions, including atrial fibrillation, myocardial infarction, and cardiac failure [see Warnings and Precautions (5.5)].

Second Primary Malignancies

Inform patients of the potential risk of developing second primary malignancies during treatment with REVLIMID [see Warnings and Precautions (5.6)].

Hepatotoxicity

Inform patients of the risk of hepatotoxicity, including hepatic failure and death, and to report any signs and symptoms associated with this event to their healthcare provider for evaluation [see Warnings and Precautions (5.8)].

Severe Cutaneous Reactions

Inform patients of the potential risk for severe skin reactions such as SJS, TEN, and DRESS and report any signs and symptoms associated with these reactions to their healthcare provider for evaluation. Patients with a prior history of Grade 4 rash associated with thalidomide treatment should not receive REVLIMID [see Warnings and Precautions (5.9)].

Tumor Lysis Syndrome

Inform patients of the potential risk of tumor lysis syndrome and to report any signs and symptoms associated with this event to their healthcare provider for evaluation [see Warnings and Precautions (5.10)].

Tumor Flare Reaction

Inform patients of the potential risk of tumor flare reaction and to report any signs and symptoms associated with this event to their healthcare provider for evaluation [see Warnings and Precautions (5.11)].

Early Mortality in Patients with MCL

Inform patients with MCL of the potential for early death [see Warnings and Precautions (5.14)].

Hypersensitivity

Inform patients of the potential for severe hypersensitivity reactions such as angioedema and anaphylaxis to REVLIMID. Instruct patients to contact their healthcare provider right away for signs and symptoms of these reactions. Advise patients to seek emergency medical attention for signs or symptoms of severe hypersensitivity reactions [see Warnings and Precautions (5.15)].

Dosing Instructions

Inform patients how to take REVLIMID [see Dosage and Administration (2)]

- REVLIMID should be taken once daily at about the same time each day,
- REVLIMID may be taken either with or without food.
- The capsules should not be opened, broken, or chewed. REVLIMID should be swallowed whole with water.
- Instruct patients that if they miss a dose of REVLIMID, they may still take it up to 12 hours after the time they would normally take it. If more than 12 hours have elapsed, they should be instructed to skip the dose for that day. The next day, they should take REVLIMID at the usual time. Warn patients to not take 2 doses to make up for the one that they missed.

Marketed by:
Bristol-Myers Squibb Company
Princeton, NJ 08543 USA

REVLIMID® is a trademark of Celgene Corporation, a Bristol-Myers Squibb company.

RevPlyPI.031/MG.031

Medication Guide

REVLIMID® (rev-li-mid)

(lenalidomide) capsules

What is the most important information I should know about REVLIMID?
Before you begin taking REVLIMID, you must read and agree to all of the instructions in the Lenalidomide REMS program. For more information, call 1-888-423-5436 or go to www.lenalidomiderems.com. Before prescribing REVLIMID, your healthcare provider will explain the Lenalidomide REMS program to you and have you sign the Patient-Physician Agreement Form.
REVLIMID may cause serious side effects including:

- Possible birth defects (deformed babies) or death of an unborn baby. Females who are pregnant or who plan to become pregnant must not take REVLIMID.
  REVLIMID is similar to the medicine thalidomide. We know thalidomide can cause severe life-threatening birth defects. REVLIMID has not been tested in pregnant females. REVLIMID has harmed unborn animals in animal testing.

Females must not get pregnant:

- For at least 4 weeks before starting REVLIMID
- While taking REVLIMID
- During any breaks (interruptions) in your treatment with REVLIMID
- For at least 4 weeks after stopping REVLIMID

Females who can become pregnant:

- Will have pregnancy tests weekly for 4 weeks, then every 4 weeks if your menstrual cycle is regular, or every 2 weeks if your menstrual cycle is irregular.
- If you miss your period or have unusual bleeding, you will need to have a pregnancy test and receive counseling.
- Must agree to use two acceptable forms of birth control at the same time, for at least 4 weeks before, while taking, during any breaks (interruptions) in your treatment, and for at least 4 weeks after stopping REVLIMID.
- Talk with your healthcare provider to find out about options for acceptable forms of birth control that you may use to prevent pregnancy before, during, and after treatment with REVLIMID.
- If you had unprotected sex or if you think your birth control has failed, stop taking REVLIMID immediately and call your healthcare provider right away.

If you become pregnant while taking REVLIMID, stop taking it right away and call your healthcare provider. If your healthcare provider is not available, you can call the REMS Call Center at 1-888-423-5436. Healthcare providers and patients should report all cases of pregnancy to:

- FDA MedWatch at 1-800-FDA-1088, and
- REMS Call Center at 1-888-423-5436

There is a pregnancy exposure registry that monitors the outcomes of females who take REVLIMID during pregnancy, or if their male partner takes REVLIMID and they are exposed during pregnancy. You can enroll in this registry by calling the REMS Call Center at the phone number listed above.

REVLIMID can pass into human semen:

- Males, including those who have had a vasectomy, must always use a latex or synthetic condom during any sexual contact with a pregnant female or a female that can become pregnant while taking REVLIMID, during any breaks (interruptions) in your treatment with REVLIMID, and for up to 4 weeks after stopping REVLIMID.
- Do not have unprotected sexual contact with a female who is or could become pregnant. Tell your healthcare provider if you do have unprotected sexual contact with a female who is or could become pregnant.
- Do not donate sperm while taking REVLIMID, during any breaks (interruptions) in your treatment, and for up to 4 weeks after stopping REVLIMID. If a female becomes pregnant with your sperm, the baby may be exposed to REVLIMID and may be born with birth defects.

Men, if your female partner becomes pregnant, you should call your healthcare provider right away.

- Low white blood cells (neutropenia) and low platelets (thrombocytopenia). REVLIMID causes low white blood cells and low platelets in most people. You may need a blood transfusion or certain medicines if your blood counts drop too low. Your healthcare provider should check your blood counts often especially during the first several months of treatment with REVLIMID, and then at least monthly. Tell your healthcare provider if you develop any bleeding or bruising, during treatment with REVLIMID.
- Blood clots. Blood clots in the arteries, veins, and lungs happen more often in people who take REVLIMID. This risk is even higher for people with multiple myeloma who take the medicine dexamethasone with REVLIMID. Heart attacks and strokes also happen more often in people who take REVLIMID with dexamethasone. To reduce this increased risk, most people who take REVLIMID will also take a blood thinner medicine.
  Before taking REVLIMID, tell your healthcare provider:
- If you have had a blood clot in the past
- If you have high blood pressure, smoke, or if you have been told you have a high level of fat in your blood (hyperlipidemia)
- About all the medicines you take. Certain other medicines can also increase your risk for blood clots
Call your healthcare provider or get medical help right away if you get any of the following during treatment with REVLIMID:
- Signs or symptoms of a blood clot in the lung, arm, or leg may include: shortness of breath, chest pain, or arm or leg swelling
- Signs or symptoms of a heart attack may include: chest pain that may spread to the arms, neck, jaw, back, or stomach area (abdomen), feeling sweaty, shortness of breath, feeling sick or vomiting
- Signs or symptoms of stroke may include: sudden numbness or weakness, especially on one side of the body, severe headache or confusion, or problems with vision, speech, or balance

What is REVLIMID?
REVLIMID is a prescription medicine, used to treat adults with:

- multiple myeloma (MM)
  - in combination with the medicine dexamethasone, or
  - as maintenance treatment after autologous hematopoietic stem cell transplantation (a type of stem cell transplant that uses your own stem cells)
- a condition called myelodysplastic syndromes (MDS). REVLIMID is for the type of MDS with a chromosome problem where part of chromosome 5 is missing. This type of MDS is known as deletion 5q MDS. People with this type of MDS may have low red blood cell counts that require treatment with blood transfusions.
- mantle cell lymphoma (MCL) when the disease comes back or becomes worse after treatment with 2 prior medicines, one of which included bortezomib. MCL is a cancer of a type of white blood cell called lymphocytes that are in the lymph nodes.
- follicular lymphoma (FL) or marginal zone lymphoma (MZL)
  - in combination with a rituximab product, and
  - who have previously been treated for their FL or MZL
FL and MZL are types of cancer of white blood cells called B-cell lymphocytes that are found in the lymph nodes and spleen.

REVLIMID should not be used to treat people who have chronic lymphocytic leukemia (CLL) unless they are participants in a controlled clinical trial.
It is not known if REVLIMID is safe and effective in children.

Who should not take REVLIMID?
Do not take REVLIMID if you:

- are pregnant, plan to become pregnant, or become pregnant during treatment with REVLIMID. See "What is the most important information I should know about REVLIMID?"
- are allergic to lenalidomide or any of the ingredients in REVLIMID. See the end of this Medication Guide for a complete list of ingredients in REVLIMID.

What should I tell my healthcare provider before taking REVLIMID?
Before you take REVLIMID, tell your healthcare provider about all of your medical conditions, including if you:

- have liver problems
- have kidney problems or receive kidney dialysis treatment
- have thyroid problems
- have had a serious skin rash with thalidomide treatment. You should not take REVLIMID.
- are lactose intolerant. REVLIMID contains lactose.
- are breastfeeding. Do not breastfeed during treatment with REVLIMID. It is not known if REVLIMID passes into your breast milk and can harm your baby.

Tell your healthcare provider about all the medicines you take, including prescription and over-the-counter medicines, vitamins, and herbal supplements. REVLIMID and other medicines may affect each other, causing serious side effects. Talk with your healthcare provider before taking any new medicines.
Know the medicines you take. Keep a list of them to show your healthcare provider and pharmacist.

How should I take REVLIMID?

- Take REVLIMID exactly as prescribed and follow all the instructions of the Lenalidomide REMS program
- Swallow REVLIMID capsules whole with water 1 time a day. Do not open, break, or chew your capsules.
- REVLIMID may be taken with or without food.
- Take REVLIMID at about the same time each day.
- Do not open or break REVLIMID capsules or handle them any more than needed.
  - If powder from the REVLIMID capsule comes in contact with your skin, wash the skin right away with soap and water.
  - If powder from the REVLIMID capsule comes in contact with the inside of your eyes, nose, or mouth, flush well with water.
- If you miss a dose of REVLIMID and it has been less than 12 hours since your regular time, take it as soon as you remember. If it has been more than 12 hours, just skip your missed dose. Do not take 2 doses at the same time.
- If you take too much REVLIMID, call your healthcare provider right away.

What should I avoid while taking REVLIMID?

- See "What is the most important information I should know about REVLIMID?"
- Females: Do not get pregnant and do not breastfeed while taking REVLIMID.
- Males: Do not donate sperm while taking REVLIMID, during any breaks (interruptions) in your treatment, and for up to 4 weeks after stopping REVLIMID.
- Do not share REVLIMID with other people. It may cause birth defects and other serious problems.
- Do not donate blood while you take REVLIMID, during any breaks (interruptions) in your treatment, and for 4 weeks after stopping REVLIMID. If someone who is pregnant gets your donated blood, her baby may be exposed to REVLIMID and may be born with birth defects.

What are the possible side effects of REVLIMID?
REVLIMID can cause serious side effects, including:

- See "What is the most important information I should know about REVLIMID?"
- Increased risk of death in people who have chronic lymphocytic leukemia (CLL). People with CLL who take REVLIMID have an increased risk of death compared with people who take the medicine chlorambucil. REVLIMID may cause you to have serious heart problems that can lead to death, including atrial fibrillation, heart attack, or heart failure. You should not take REVLIMID if you have CLL unless you are participating in a controlled clinical trial.
- Risk of new cancers (malignancies). An increase in new (second) cancers has happened in patients who received REVLIMID and melphalan, or a blood stem cell transplant, including certain blood cancers, such as acute myelogenous leukemia (AML), and myelodysplastic syndrome (MDS) and certain other types of cancers of the skin and other organs. Talk with your healthcare provider about your risk of developing new cancers if you take REVLIMID. Your healthcare provider will check you for new cancers during your treatment with REVLIMID.
- Severe liver problems, including liver failure and death. Your healthcare provider should do blood tests to check your liver function during your treatment with REVLIMID. Tell your healthcare provider right away if you develop any of the following symptoms of liver problems:

- yellowing of your skin or the white part of your eyes (jaundice)
- dark or brown (tea-colored) urine

- pain on the upper right side of your stomach area (abdomen)
- bleeding or bruising more easily than normal
- feeling very tired

- Severe skin reactions and severe allergic reactions can happen with REVLIMID and may cause death.

Call your healthcare provider right away if you develop any of the following signs or symptoms during treatment with REVLIMID:

- a red, itchy, skin rash

- peeling of your skin or blisters

- severe itching
- fever

Get emergency medical help right away if you develop any of the following signs or symptoms during treatment with REVLIMID:

- swelling of your lips, mouth, tongue, or throat
- trouble breathing or swallowing

- raised red areas on your skin (hives)
- a very fast heartbeat
- you feel dizzy or faint

- Tumor lysis syndrome (TLS). TLS is caused by the fast breakdown of cancer cells. TLS can cause kidney failure and the need for dialysis treatment, abnormal heart rhythm, seizure and sometimes death. Your healthcare provider may do blood tests to check you for TLS.
- Worsening of your tumor (tumor flare reaction) can happen with REVLIMID and may cause death. Tell your healthcare provider if you get any of these symptoms of tumor flare reaction during treatment with REVLIMID: tender swollen lymph nodes, low grade fever, pain, or rash.

Your healthcare provider may tell you to decrease your dose, temporarily stop or permanently stop taking REVLIMID if you develop certain serious side effects during treatment with REVLIMID.

- Thyroid problems. Your healthcare provider may check your thyroid function before you start taking REVLIMID and during treatment with REVLIMID.
- Risk of Early Death in MCL. In people who have Mantle Cell Lymphoma (MCL), there may be a risk of dying sooner (early death) when taking REVLIMID. Talk with your healthcare provider about any concerns and possible risk factors.

The most common side effects of REVLIMID include:

- diarrhea
- rash
- nausea
- constipation
- tiredness or weakness
- fever
- itching

- swelling of your arms, hands, legs, feet and skin
- sleep problems (insomnia)
- headache
- muscle cramps or spasms
- shortness of breath
- cough, sore throat, and other symptoms of a cold

- upper respiratory tract infection or bronchitis
- inflammation of the stomach and intestine ("stomach flu")
- nose bleed
- shaking or trembling (tremor)
- joint aches
- pain in your back or stomach-area (abdomen)

These are not all the possible side effects of REVLIMID.
Call your doctor for medical advice about side effects. You may report side effects to the FDA at 1-800-FDA-1088.

How should I store REVLIMID?

- Store REVLIMID at room temperature between 68°F to 77°F (20°C to 25°C).
- Return any unused REVLIMID to Bristol-Myers Squibb or your healthcare provider.

Keep REVLIMID and all medicines out of the reach of children.

General information about the safe and effective use of REVLIMID.
Medicines are sometimes prescribed for purposes other than those listed in a Medication Guide. Do not take REVLIMID for conditions for which it was not prescribed. Do not give REVLIMID to other people, even if they have the same symptoms you have. It may harm them and may cause birth defects.
If you would like more information, talk with your healthcare provider. You can ask your healthcare provider or pharmacist for information about REVLIMID that is written for health professionals.

For more information, call 1-888-423-5436 or go to www.lenalidomiderems.com.

What are the ingredients in REVLIMID?
Active ingredient: lenalidomide
Inactive ingredients: lactose anhydrous, microcrystalline cellulose, croscarmellose sodium, and magnesium stearate.
The 5 mg and 25 mg capsule shell contains gelatin, titanium dioxide and black ink.
The 2.5 and 10 mg capsule shell contains gelatin, FD&C blue #2, yellow iron oxide, titanium dioxide and black ink.
The 15 mg capsule shell contains gelatin, FD&C blue #2, titanium dioxide and black ink.
The 20 mg capsule shell contains gelatin, FD&C blue #2, yellow iron oxide, titanium dioxide and black ink.
Marketed by: Bristol-Myers Squibb Company, Princeton, NJ 08543 USA
REVLIMID® is a trademark of Celgene Corporation, a Bristol-Myers Squibb company.
REVPlyMG.031 3/2023

This Medication Guide has been approved by the U.S. Food and Drug Administration. Revised: MAR 2023

PACKAGE/LABEL PRINCIPAL DISPLAY PANEL

NDC 59572-402-28

Revlimid

(lenalidomide) Capsules

2.5 mg

WARNING: POTENTIAL FOR HUMAN BIRTH DEFECTS.

Rx Only

28 Capsules

PACKAGE/LABEL PRINCIPAL DISPLAY PANEL

NDC 59572-405-28

Revlimid

(lenalidomide) Capsules

5 mg

WARNING: POTENTIAL FOR HUMAN BIRTH DEFECTS.

Rx Only

28 Capsules

PACKAGE/LABEL PRINCIPAL DISPLAY PANEL

NDC 59572-410-28

Revlimid

(lenalidomide) Capsules

10 mg

WARNING: POTENTIAL FOR HUMAN BIRTH DEFECTS.

Rx Only

28 Capsules

PACKAGE/LABEL PRINCIPAL DISPLAY PANEL

NDC 59572-415-21

Revlimid

(lenalidomide) Capsules

15 mg

WARNING: POTENTIAL FOR HUMAN BIRTH DEFECTS.

Rx Only

21 Capsules

PACKAGE/LABEL PRINCIPAL DISPLAY PANEL

NDC 59572-420-21

Revlimid

(lenalidomide) Capsules

20 mg

WARNING: POTENTIAL FOR HUMAN BIRTH DEFECTS.

Rx Only

21 Capsules

PACKAGE/LABEL PRINCIPAL DISPLAY PANEL

NDC 59572-425-21

Revlimid

(lenalidomide) Capsules

25 mg

WARNING: POTENTIAL FOR HUMAN BIRTH DEFECTS.

Rx Only

21 Capsules